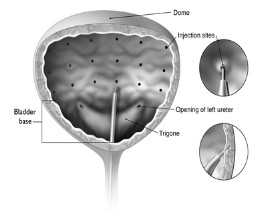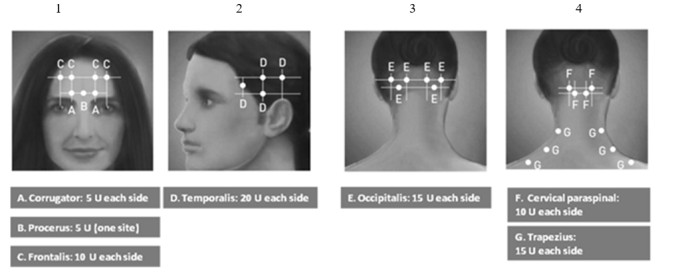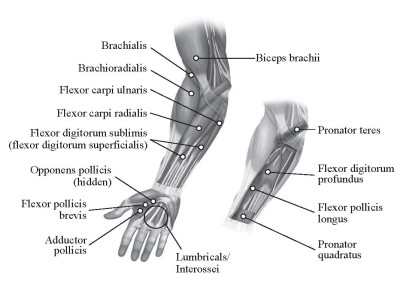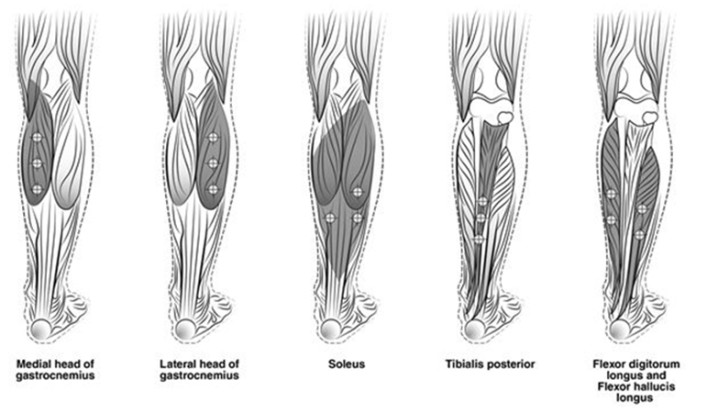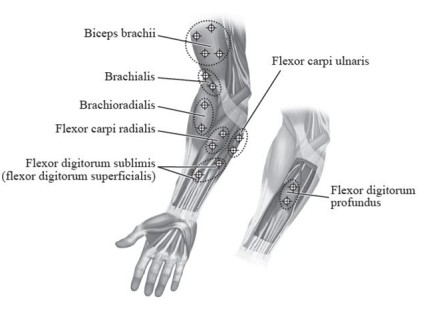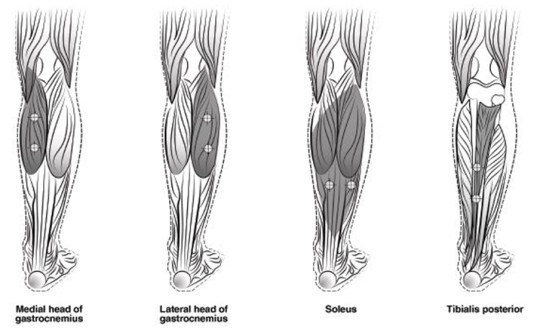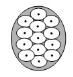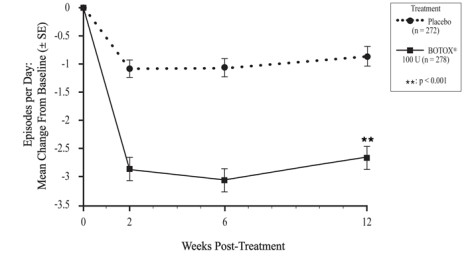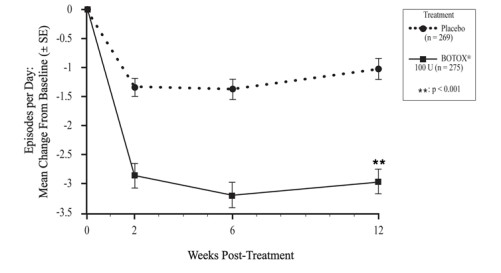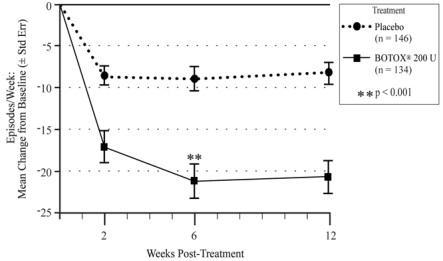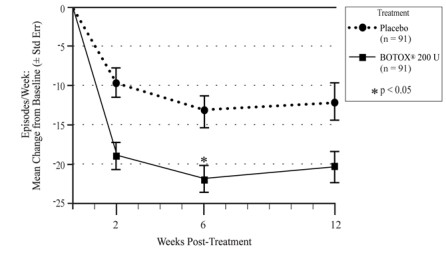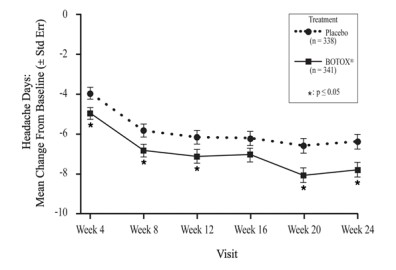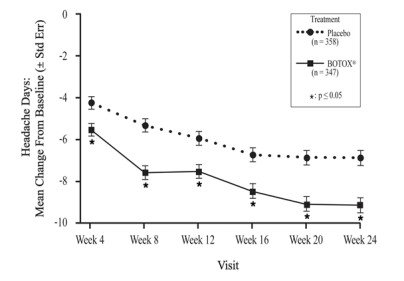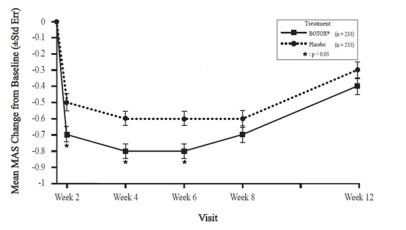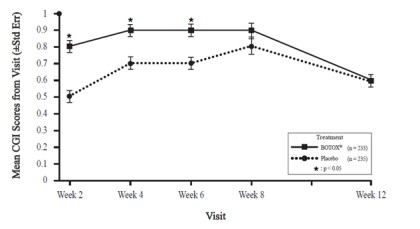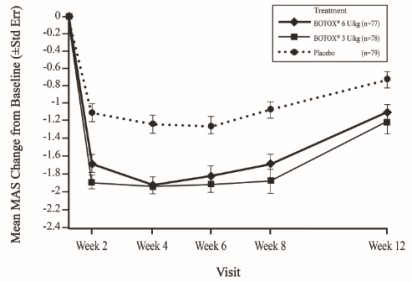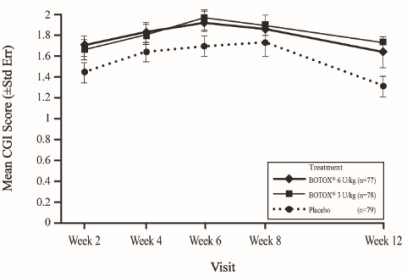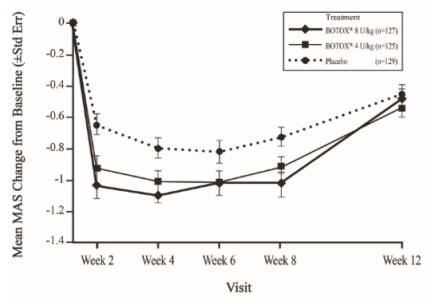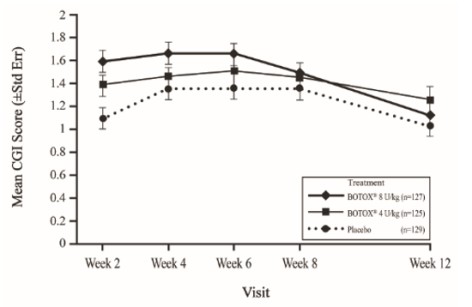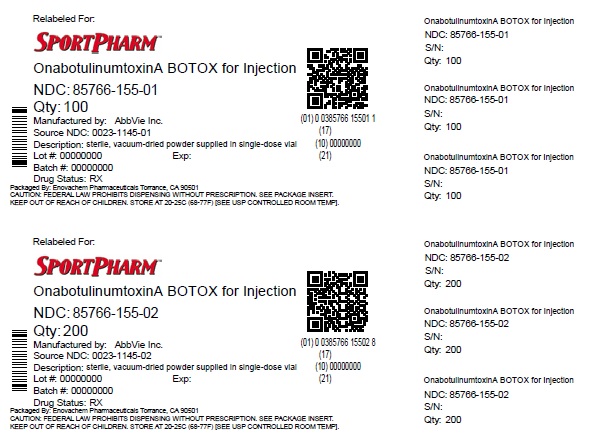 DRUG LABEL: BOTOX
NDC: 85766-155 | Form: INJECTION, POWDER, LYOPHILIZED, FOR SOLUTION
Manufacturer: Sportpharm LLC
Category: prescription | Type: HUMAN PRESCRIPTION DRUG LABEL
Date: 20260202

ACTIVE INGREDIENTS: BOTULINUM TOXIN TYPE A 100 [USP'U]/1 1
INACTIVE INGREDIENTS: ALBUMIN HUMAN 0.5 mg/1 1; SODIUM CHLORIDE 0.9 mg/1 1

HIGHLIGHTS OF PRESCRIBING INFORMATION

These highlights do not include all the information needed to use BOTOX® safelyand effectively. See full prescribing information for BOTOX.
BOTOX® (onabotulinumtoxinA) for injection, for intramuscular, intradetrusor, or intradermal use
Initial U.S. Approval: 1989

WARNING: DISTANT SPREAD OF TOXIN EFFECT

See full prescribing information for complete boxed warning.

The effects of BOTOX and all botulinum toxin products may spread from the area of injection to produce symptoms consistent with botulinum toxin effects. These symptoms have been reported hours to weeks after injection. Swallowing and breathing difficulties can be life threatening and there have been reports of death. The risk of symptoms is probably greatest in children treated for spasticity but symptoms can also occur in adults, particularly in those patients who have an underlying condition that would predispose them to these symptoms. (5.1)

1 INDICATIONS AND USAGE

BOTOX is an acetylcholine release inhibitor and a neuromuscular blocking agent indicated for:

- Treatment of overactive bladder (OAB) with symptoms of urge urinary incontinence, urgency, and frequency, in adults who have an inadequate response to or are intolerant of an anticholinergic medication (1.1)
- Treatment of urinary incontinence due to detrusor overactivity associated with a neurologic condition [e.g., spinal cord injury (SCI), multiple sclerosis (MS)] in adults who have an inadequate response to or are intolerant of an anticholinergic medication (1.1)
- Treatment of neurogenic detrusor overactivity (NDO) in pediatric patients 5 years of age and older who have an inadequate response to or are intolerant of anticholinergic medication. (1.2)
- Prophylaxis of headaches in adult patients with chronic migraine (≥15 days per month with headache lasting 4 hours a day or longer) (1.3)
- Treatment of spasticity in patients 2 years of age and older (1.4)
- Treatment of cervical dystonia in adult patients, to reduce the severity of abnormal head position and neck pain (1.5)
- Treatment of severe axillary hyperhidrosis that is inadequately managed by topical agents in adult patients (1.6)
- Treatment of blepharospasm associated with dystonia in patients 12 years of age and older (1.7)
- Treatment of strabismus in patients 12 years of age and older (1.7)

Limitationsof Use

Safety and effectiveness of BOTOX have not been established for:

- Prophylaxis of episodic migraine (14 headache days or fewer per month) (1.3)
- Treatment of hyperhidrosis in body areas other than axillary (1.6)

2 DOSAGE AND ADMINISTRATION

- Follow indication-specific dosage and administration recommendations.
  In a 3 month interval, do not exceed a total dose of:
  • Adults: 400 Units
  • Pediatrics: the lesser of 10 Units/kg or 340 Units (2.1)
- See Preparation and Dilution Technique for instructions on BOTOX reconstitution, storage, and preparation before injection (2.2)
- Overactive Bladder: Recommended total dose 100 Units, as 0.5 mL (5 Units) injections across 20 sites into the detrusor (2.3)
- Adult Detrusor Overactivity associated with a Neurologic Condition: Recommended total dose 200 Units, as 1 mL (~6.7 Units) injections across 30 sites into the detrusor (2.3)
- Pediatric Detrusor Overactivity associated with a Neurologic Condition: 0.5 mL injections across 20 sites into the detrusor (2.4)
  • Greater than or equal to 34 kg: Recommended total dose is 200 Units
  • Less than 34 kg: Recommended total dose is 6 Units/kg
- Chronic Migraine: Recommended total dose 155 Units, as 0.1 mL (5 Units) injections per each site divided across 7 head/neck muscles (2.5)
- Adult Upper Limb Spasticity: Recommended total dose up to 400 Units divided among affected muscles (2.6)
- Adult Lower Limb Spasticity: Recommended total dose 300 Units to 400 Units divided across ankle and toe muscles (2.6)
- Pediatric Upper Limb Spasticity: Recommended total dose 3 Units/kg to 6 Units/kg (maximum 200 Units) divided among affected muscles (2.7)
- Pediatric Lower Limb Spasticity: Recommended total dose 4 Units/kg to 8 Units/kg (maximum 300 Units) divided among affected muscles (2.7)
- Cervical Dystonia: Base dosing on the patient’s head and neck position, localization of pain, muscle hypertrophy, patient response, and adverse event history; use lower initial dose in botulinum toxin naïve patients (2.8)
- Axillary Hyperhidrosis: 50 Units per axilla (2.9)
- Blepharospasm: 1.25 Units-2.5 Units into each of 3 sites per affected eye (2.10)
- Strabismus: The dose is based on prism diopter correction or previous response to treatment with BOTOX (2.11)

3 DOSAGE FORMS AND STRENGTHS

For Injection: 100 Units vacuum-dried powder in a single-dose vial (3)

4 CONTRAINDICATIONS

- Hypersensitivity to any botulinum toxin preparation or to any of the components in the formulation (4, 5.4, 6)
- Infection at the proposed injection site (4)
- Intradetrusor Injections: Urinary tract infection or urinary retention (4)

5 WARNINGS AND PRECAUTIONS

- Spread of toxin effects; swallowing and breathing difficulties can lead to death. Seek immediate medical attention if respiratory, speech or swallowing difficulties occur (5.1, 5.6)
- Potency Units of BOTOX are not interchangeable with other preparations of botulinum toxin products (5.2, 11)
- Potential serious adverse reactions after BOTOX injections for unapproved uses (5.3)
- Concomitant neuromuscular disorder may exacerbate clinical effects of treatment (5.5)
- Use with caution in patients with compromised respiratory function (5.6, 5.7, 5.10)
- Corneal exposure and ulceration due to reduced blinking may occur with BOTOX treatment of blepharospasm (5.8)
- Retrobulbar hemorrhages and compromised retinal circulation may occur with BOTOX treatment of strabismus (5.9)
- Bronchitis and upper respiratory tract infections in patients treated for spasticity (5.10)
- Urinary tract infections in patients treated for OAB (5.12)
- Urinary retention: Post-void residual urine volume should be monitored in patients treated for OAB or adult detrusor overactivity associated with a neurologic condition who do not catheterize routinely, particularly patients with multiple sclerosis or diabetes mellitus. (5.13)

6 ADVERSE REACTIONS

The most common adverse reactions (≥5% and >placebo, if applicable) are (6.1):

- OAB: urinary tract infection, dysuria, urinary retention
- Adult Detrusor Overactivity associated with a neurologic condition: urinary tract infection, urinary retention
- Pediatric Detrusor Overactivity associated with a neurologic condition: urinary tract infection, leukocyturia, bacteriuria
- Chronic Migraine: neck pain, headache
- Adult Spasticity: pain in extremity
- Pediatric Spasticity: upper respiratory tract infection
- Cervical Dystonia: dysphagia, upper respiratory infection, neck pain, headache, increased cough, flu syndrome, back pain, rhinitis
- Axillary Hyperhidrosis: injection site pain and hemorrhage, non-axillary sweating, pharyngitis, flu syndrome

To report SUSPECTED ADVERSE REACTIONS, contact AbbVie at 1-800-678-1605 or FDA at 1-800-FDA-1088 or www.fda.gov/medwatch.

7 DRUG INTERACTIONS

Patients receiving concomitant treatment of BOTOX and aminoglycosides or other agents interfering with neuromuscular transmission (e.g., curare-like agents), or muscle relaxants, should be observed closely because the effect of BOTOX may be potentiated (7.1, 7.4)

8 USE IN SPECIFIC POPULATIONS

- Pregnancy: Based on animal data, may cause fetal harm. (8.1)

FULL PRESCRIBING INFORMATION

WARNING: DISTANT SPREAD OF TOXIN EFFECT

Postmarketing reports indicate that the effects of BOTOX and all botulinum toxin products may spread from the area of injection to produce symptoms consistent with botulinum toxin effects. These may include asthenia, generalized muscle weakness, diplopia, ptosis, dysphagia, dysphonia, dysarthria, urinary incontinence and breathing difficulties. These symptoms have been reported hours to weeks after injection. Swallowing and breathing difficulties can be life threatening and there have been reports of death. The risk of symptoms is probably greatest in children treated for spasticity but symptoms can also occur in adults treated for spasticity and other conditions, particularly in those patients who have an underlying condition that would predispose them to these symptoms. In unapproved usesand in approved indications, cases of spread of effect have been reported at doses comparable to those used to treat cervical dystonia and spasticity and at lower doses [see Warnings and Precautions (5.1)].

1 INDICATIONS AND USAGE

1.1 Adult Bladder Dysfunction

Overactive Bladder

BOTOX for injection is indicated for the treatment of overactive bladder with symptoms of urge urinary incontinence, urgency, and frequency, in adults who have an inadequate response to or are intolerant of an anticholinergic medication.

Detrusor Overactivity associated with a Neurologic Condition

BOTOX is indicated for the treatment of urinary incontinence due to detrusor overactivity associated with a neurologic condition (e.g., SCI, MS) in adults who have an inadequate response to or are intolerant of an anticholinergic medication.

1.2 Pediatric Detrusor Overactivity Associated with a Neurologic Condition

BOTOX is indicated for the treatment of neurogenic detrusor overactivity (NDO) in pediatric patients 5 years of age and older who have an inadequate response to or are intolerant of anticholinergic medication.

1.3 Chronic Migraine

BOTOX is indicated for the prophylaxis of headaches in adult patients with chronic migraine (≥15 days per month with headache lasting 4 hours a day or longer).

Limitations of Use

Safety and effectiveness have not been established for the prophylaxis of episodic migraine (14 headache days or fewer per month) in seven placebo-controlled studies.

1.4 Spasticity

BOTOX is indicated for the treatment of spasticity in patients 2 years of age and older.

Limitations of Use

BOTOX has not been shown to improve upper extremity functional abilities, or range of motion at a joint affected by a fixed contracture.

1.5 Cervical Dystonia

BOTOX is indicated for the treatment of adults with cervical dystonia, to reduce the severity of abnormal head position and neck pain associated with cervical dystonia.

1.6 Primary Axillary Hyperhidrosis

BOTOX is indicated for the treatment of severe primary axillary hyperhidrosis that is inadequately managed with topical agents.

Limitations of Use
The safety and effectiveness of BOTOX for hyperhidrosis in other body areas have not been established. Weakness of hand muscles and blepharoptosis may occur in patients who receive BOTOX for palmar hyperhidrosis and facial hyperhidrosis, respectively. Patients should be evaluated for potential causes of secondary hyperhidrosis (e.g., hyperthyroidism) to avoid symptomatic treatment of hyperhidrosis without the diagnosis and/or treatment of the underlying disease.

Safety and effectiveness of BOTOX have not been established for the treatment of axillary hyperhidrosis in pediatric patients under age 18.

1.7 Blepharospasm and Strabismus

BOTOX is indicated for the treatment of strabismus and blepharospasm associated with dystonia, including benign essential blepharospasm or VII nerve disorders in patients 12 years of age and older.

2 DOSAGE AND ADMINISTRATION

2.1 Instructions for Safe Use

The potency Units of BOTOX (onabotulinumtoxinA) for injection are specific to the preparation and assay method utilized. They are not interchangeable with other preparations of botulinum toxin products and, therefore, units of biological activity of BOTOX cannot be compared to nor converted into units of any other botulinum toxin products assessed with any other specific assay method [see Warnings and Precautions (5.2) and Description (11)].

Indication specific dosage and administration recommendations should be followed. When initiating treatment, the lowest recommended dose should be used. In treating adult patients for one or more indications, the maximum cumulative dose should not exceed 400 Units, in a 3-month interval. In pediatric patients, the total dose should not exceed the lower of 10 Units/kg body weight or 340 Units, in a 3-month interval [see Dosage and Administration (2.7)].

The safe and effective use of BOTOX depends upon proper storage of the product, selection of the correct dose, and proper reconstitution and administration techniques. An understanding of standard electromyographic techniques is also required for treatment of strabismus, upper or lower limb spasticity, and may be useful for the treatment of cervical dystonia. Physicians administering BOTOX must understand the relevant neuromuscular and structural anatomy of the area involved and any alterations to the anatomy due to prior surgical procedures and disease, especially when injecting near the lungs.

Do not use BOTOX and contact AbbVie (1-800-678-1605) if:

- the tamper evident features on the carton appear to be broken or compromised, or
- the U.S. License number 1889 is not present on the vial label and carton labeling [see How Supplied/Storage and Handling (16)].

2.2 Preparation and Dilution Technique

Prior to injection, reconstitute each vacuum-dried vial of BOTOX with only sterile, preservative-free 0.9% Sodium Chloride Injection, USP. Draw up the proper amount of diluent in the appropriate size syringe (see Table 1, or for specific instructions for detrusor overactivity associated with a neurologic condition, see Section 2.3), and slowly inject the diluent into the vial. Discard the vial if a vacuum does not pull the diluent into the vial. Gently mix BOTOXwith the diluent by rotating the vial. Record the date and time of reconstitution on the space on the label. BOTOX should be administered within 24 hours after reconstitution. During this time period, unused reconstituted BOTOX should be stored in a refrigerator (2° to 8°C) for up to 24 hours until time of use. BOTOX vials are for single-dose only. Discard any unused portion.

Table 1: Dilution Instructions for BOTOX Vials (100 Units and 200 Units)**
Diluent* Added to 100 Unit Vial | Resulting Dose Units per 0.1 mL | Diluent* Added to 200 Unit Vial | Resulting Dose Units per 0.1 mL
1 mL 2 mL 4 mL 8 mL 10 mL | 10 Units 5 Units 2.5 Units 1.25 Units 1 Unit | 1 mL 2 mL 4 mL 8 mL 10 mL | 20 Units 10 Units 5 Units 2.5 Units 2 Units

*Preservative-free 0.9% Sodium Chloride Injection, USP Only

**For Detrusor Overactivity associated with a Neurologic Condition Dilution, see Section 2.3

Note: These dilutions are calculated for an injection volume of 0.1 mL. A decrease or increase in the BOTOX dose is also possible by administering a smaller or larger injection volume - from 0.05 mL (50% decrease in dose) to 0.15 mL (50% increase in dose).

An injection of BOTOX is prepared by drawing into an appropriately sized sterile syringe an amount of the properly reconstituted toxin slightly greater than the intended dose. Air bubbles in the syringe barrel are expelled and the syringe is attached to an appropriate injection needle. Patency of the needle should be confirmed. A new, sterile needle and syringe should be used to enter the vial on each occasion for removal of BOTOX.

Reconstituted BOTOX should be clear, colorless, and free of particulate matter. Parenteral drug products should be inspected visually for particulate matter and discoloration prior to administration and whenever the solution and the container permit.

2.3 Adult Bladder Dysfunction

General

Patients must not have a urinary tract infection (UTI) at the time of treatment. Prophylactic antibiotics, except aminoglycosides, [see Drug Interactions (7.1)]should be administered 1-3 days pre-treatment, on the treatment day, and 1-3 days post-treatment to reduce the likelihood of procedure-related UTI.

Patients should discontinue anti-platelet therapy at least 3 days before the injection procedure. Patients on anti-coagulant therapy need to be managed appropriately to decrease the risk of bleeding.

Appropriate caution should be exercised when performing a cystoscopy.

Overactive Bladder

An intravesical instillation of diluted local anesthetic with or without sedation may be used prior to injection, per local site practice. If a local anesthetic instillation is performed, the bladder should be drained and irrigated with sterile saline before injection.

The recommended dose is 100 Units of BOTOX, and is the maximum recommended dose. The recommended dilution is 100 Units/10 mL with preservative-free 0.9% Sodium Chloride Injection, USP (see Table 1). Dispose of any unused saline.

Reconstituted BOTOX (100 Units/10 mL) is injected into the detrusor muscle via a flexible or rigid cystoscope, avoiding the trigone. The bladder should be instilled with enough saline to achieve adequate visualization for the injections, but over-distension should be avoided.

The injection needle should be filled (primed) with approximately 1 mL of reconstituted BOTOX prior to the start of injections (depending on the needle length) to remove any air.

The needle should be inserted approximately 2 mm into the detrusor, and 20 injections of 0.5 mL each (total volume of 10 mL) should be spaced approximately 1 cm apart (see Figure 1). For the final injection, approximately 1 mL of sterile normal saline should be injected so that the remaining BOTOX in the needle is delivered to the bladder. After the injections are given, patients should demonstrate their ability to void prior to leaving the clinic. The patient should be observed for at least 30 minutes post-injection and until a spontaneous void has occurred.

Patients should be considered for reinjection when the clinical effect of the previous injection has diminished (median time until patients qualified for the second treatment of BOTOX in double-blind, placebo-controlled clinical studies was 169 days [~24 weeks]), but no sooner than 12 weeks from the prior bladder injection.

Figure 1: Injection Pattern for Intradetrusor Injections for Treatment of Overactive Bladder and Detrusor Overactivity Associatedwith a Neurologic Condition

Detrusor Overactivity associated with a Neurologic Condition

An intravesical instillation of diluted local anesthetic with or without sedation, or general anesthesia may be used prior to injection, per local site practice. If a local anesthetic instillation is performed, the bladder should be drained and irrigated with sterile saline before injection.

The recommended dose is 200 Units of BOTOX per treatment, and should not be exceeded.

200 Unit Vial of BOTOX

- Reconstitute a 200 Unit vial of BOTOX with 6 mL of preservative-free 0.9% Sodium Chloride Injection, USP and mix the vial gently.
- Draw 2 mL from the vial into each of three 10 mL syringes.
- Complete the reconstitution by adding 8 mL of preservative-free 0.9% Sodium Chloride Injection, USP into each of the 10 mL syringes, and mix gently. This will result in three 10 mL syringes each containing 10 mL (~67 Units in each), for a total of 200 Units of reconstituted BOTOX.
- Use immediately after reconstitution in the syringe. Dispose of any unused saline.

100 Unit Vial of BOTOX

- Reconstitute two 100 Unit vials of BOTOX, each with 6 mL of preservative-free 0.9% Sodium Chloride Injection, USP and mix the vials gently.
- Draw 4 mL from each vial into each of two 10 mL syringes. Draw the remaining 2 mL from each vial into a third 10 mL syringe for a total of 4 mL in each syringe.
- Complete the reconstitution by adding 6 mL of preservative-free 0.9% Sodium Chloride Injection, USP into each of the 10 mL syringes, and mix gently. This will result in three 10 mL syringes each containing 10 mL (~67 Units in each), for a total of 200 Units of reconstituted BOTOX.
- Use immediately after reconstitution in the syringe. Dispose of any unused saline.

Reconstituted BOTOX (200 Units/30 mL) is injected into the detrusor muscle via a flexible or rigid cystoscope, avoiding the trigone. The bladder should be instilled with enough saline to achieve adequate visualization for the injections, but over-distension should be avoided.

The injection needle should be filled (primed) with approximately 1 mL of reconstituted BOTOX prior to the start of injections (depending on the needle length) to remove any air.

The needle should be inserted approximately 2 mm into the detrusor, and 30 injections of 1 mL (~6.7 Units) each (total volume of 30 mL) should be spaced approximately 1 cm apart (see Figure 1). For the final injection, approximately 1 mL of sterile normal saline should be injected so that the remaining BOTOX in the needle is delivered to the bladder. After the injections are given, the saline used for bladder wall visualization should be drained. The patient should be observed for at least 30 minutes post-injection.

Patients should be considered for re-injection when the clinical effect of the previous injection diminishes (median time to qualification for re-treatment in the double-blind, placebo-controlled clinical studies was 295-337 days [42-48 weeks] for BOTOX 200 Units), but no sooner than 12 weeks from the prior bladder injection.

2.4 Pediatric Detrusor Overactivity Associatedwith a Neurologic Condition

Patients must not have a urinary tract infection (UTI) at the time of treatment. Oral prophylactic antibiotics, except aminoglycosides, [see Drug Interactions (7.1)]should be administered 1-3 days pre-treatment, on the treatment day, and 1-3 days post-treatment to reduce the likelihood of procedure-related UTI. Alternatively, for patients receiving general anesthesia (or conscious sedation) for the treatment of detrusor overactivity associated with a neurologic condition, one dose of IV prophylactic antibiotics, except aminoglycosides, [see Drug Interactions (7.1)]may be administered prior to treatment administration on the day of treatment.

Patients should discontinue anti-platelet therapy at least 3 days before the injection procedure. Patients on anti-coagulant therapy need to be managed appropriately to decrease the risk of bleeding.

Appropriate caution should be exercised when performing a cystoscopy.

- In patients 5 years to less than 12 years of age: Consider general anesthesia (or conscious sedation) prior to injection, per local site practice.
- In patients 12 years of age or older: Consider an intravesical instillation of diluted local anesthetic with or without sedation, or general anesthesia prior to injection, per local site practice.

At a minimum, consider a diluted instillation of local anesthetic for all age groups. If a local anesthetic instillation is performed, drain and irrigate the bladder with sterile saline before injection.

If patient’s body weight is greater than or equal to 34 kg, the recommended dosage is 200 Units of BOTOX per treatment administered as an intradetrusor injection after dilution:

- Reconstitute BOTOX to result in 20 Units BOTOX/mL in the vial(s):
  ◦ BOTOX 200 Unit vial: add 10 mL of preservative-free 0.9% Sodium Chloride Injection, USP and mix the vial gently.
  ◦ BOTOX 100 Unit vials: add 5 mL of preservative-free 0.9% Sodium Chloride Injection, USP to each of two 100 Unit vials of BOTOX and mix the vials gently.
- Draw 10 mL from the vial(s) into one 10 mL dosing syringe.
- Use immediately after reconstitution in the syringe. Dispose of any unused saline.

If patient’s body weight is less than 34 kg, the recommended dosage is 6 Units/kg body weight administered as a bladder injection after dilution (refer to Table 2):

- Reconstitute BOTOX to result in 20 Units BOTOX/mL in the vial(s):
  ◦ BOTOX 200 Unit vial: add 10 mL of preservative-free 0.9% Sodium Chloride Injection, USP and mix the vial gently.
  ◦ BOTOX 100 Unit vial(s): add 5 mL of preservative-free 0.9% Sodium Chloride Injection, USP to one 100 Unit vial of BOTOX (if final dose is less than or equal to 100 U) or to each of two 100 Unit vials of BOTOX (if final dose is greater than 100 U) and mix the vial(s) gently.
- Refer to Table 2 for dilution instructions (i.e., the amount of reconstituted BOTOX and additional diluent to draw into one 10 mL dosing syringe).
- Use BOTOX immediately after reconstitution in the syringe. Dispose of any unused preservative-free 0.9% Sodium Chloride Injection, USP.

Table 2: BOTOX Dilution Instructions and Final Dosing for Patients with Body Weight < 34 kg
Body Weight (kg) | Volume of reconstituted BOTOX and Diluent*(mL) to draw into dosing syringe to achieve a final volume of 10 mL |  | Final dose of BOTOXin dosing syringe
 | BOTOX (mL) | Diluent* (mL)
12 to less than 14 | 3.6 | 6.4 | 72 Units
14 to less than 16 | 4.2 | 5.8 | 84 Units
16 to less than 18 | 4.8 | 5.2 | 96 Units
18 to less than 20 | 5.4 | 4.6 | 108 Units
20 to less than 22 | 6 | 4 | 120 Units
22 to less than 24 | 6.6 | 3.4 | 132 Units
24 to less than 26 | 7.2 | 2.8 | 144 Units
26 to less than 28 | 7.8 | 2.2 | 156 Units
28 to less than 30 | 8.4 | 1.6 | 168 Units
30 to less than 32 | 9 | 1 | 180 Units
32 to less than 34 | 9.6 | 0.4 | 192 Units

*Preservative-free 0.9% Sodium Chloride Injection, USP Only

Reconstituted BOTOX is injected into the detrusor muscle via a flexible or rigid cystoscope, avoiding the trigone. The bladder should be instilled with enough saline to achieve adequate visualization for the injections, but over-distension should be avoided.

The injection needle should be filled (primed) with approximately 1 mL of reconstituted BOTOX prior to the start of injections (depending on the needle length) to remove any air.

The needle should be inserted approximately 2 mm into the detrusor, and 20 injections of 0.5 mL each (total volume of 10 mL) should be spaced approximately 1 cm apart (see Figure 1). For the final injection, approximately 1 mL of sterile normal saline should be injected so that the remaining BOTOX in the needle is delivered to the bladder. After the injections are given, the saline used for bladder wall visualization should be drained. The patient should be observed for at least 30 minutes post-injection.

Patients should be considered for re-injection when the clinical effect of the previous injection diminishes (median time to qualification for re-treatment in the double-blind, parallel group clinical study was 207 days [30 weeks] for BOTOX 200 Units), but no sooner than 12 weeks from the prior bladder injection.

2.5 Chronic Migraine

The recommended dilution is 200 Units/4 mL or 100 Units/2 mL, with a final concentration of 5 Units per 0.1 mL (see Table 1). The recommended dose for treating chronic migraine is 155 Units administered intramuscularly using a sterile 30-gauge, 0.5 inch needle as 0.1 mL (5 Units) injections per each site. Injections should be divided across 7 specific head/neck muscle areas as specified in the diagrams and Table 3 below. A one inch needle may be needed in the neck region for patients with thick neck muscles. With the exception of the procerus muscle, which should be injected at one site (midline), all muscles should be injected bilaterally with half the number of injection sites administered to the left, and half to the right side of the head and neck. The recommended re-treatment schedule is every 12 weeks.

Diagrams 1-4: Recommended Injection Sites (Athrough G) for Chronic Migraine

Table 3: BOTOX Dosing by Muscle for Chronic Migraine
Head/Neck Area | Recommended Dose (Number of Sitesa)
Frontalisb | 20 Units divided in 4 sites
Corrugatorb | 10 Units divided in 2 sites
Procerus | 5 Units in 1 site
Occipitalisb | 30 Units divided in 6 sites
Temporalisb | 40 Units divided in 8 sites
Trapeziusb | 30 Units divided in 6 sites
Cervical Paraspinal Muscle Groupb | 20 Units divided in 4 sites
Total Dose: | 155 Unitsdivided in 31 sites

aEach IM injection site = 0.1 mL = 5 Units BOTOX

bDose distributed bilaterally

2.6 Adult Spasticity

General

Dosing in initial and sequential treatment sessions should be tailored to the individual based on the size, number and location of muscles involved, severity of spasticity, the presence of local muscle weakness, the patient’s response to previous treatment, or adverse event history with BOTOX.

The recommended dilution is 200 Units/4 mL or 100 Units/2 mL with preservative-free 0.9% Sodium Chloride Injection, USP (see Table 1). The lowest recommended starting dose should be used, and no more than 50 Units per site should generally be administered. An appropriately sized needle (e.g., 25-30 gauge) may be used for superficial muscles, and a longer 22 gauge needle may be used for deeper musculature. Localization of the involved muscles with techniques such as needle electromyographic guidance, nerve stimulation, or ultrasound is recommended.

Repeat BOTOX treatment may be administered when the effect of a previous injection has diminished, but generally no sooner than 12 weeks after the previous injection. The degree and pattern of muscle spasticity at the time of re-injection may necessitate alterations in the dose of BOTOX and muscles to be injected.

Adult Upper Limb Spasticity

In clinical trials, doses ranging from 75 Units to 400 Units were divided among selected muscles (see Table 4and Figure 2) at a given treatment session.

Table 4: BOTOX Dosing by Muscle for Adult Upper Limb Spasticity
Muscle | Recommended Dose Total Dosage (Number of Sites)
Biceps Brachii | 60 Units to 200 Units divided in 2 to 4 sites
Brachioradialis | 45 Units to 75 Units divided in 1 to 2 sites
Brachialis | 30 Units to 50 Units divided in 1 to 2 sites
Pronator Teres | 15 Units to 25 Units in 1 site
Pronator Quadratus | 10 Units to 50 Units in 1 site
Flexor Carpi Radialis | 12.5 Units to 50 Units in 1 site
Flexor Carpi Ulnaris | 12.5 Units to 50 Units in 1 site
Flexor Digitorum Profundus | 30 Units to 50 Units in 1 site
Flexor Digitorum Sublimis | 30 Units to 50 Units in 1 site
Lumbricals/Interossei | 5 Units to 10 Units in 1 site
Adductor Pollicis | 20 Units in 1 site
Flexor Pollicis Longus | 20 Units in 1 site
Flexor pollicis brevis/ Opponens pollicis | 5 Units to 25 Units in 1 site

Figure 2: Injection Sites for Adult Upper Limb Spasticity

Adult Lower Limb Spasticity

The recommended dose for treating adult lower limb spasticity is 300 Units to 400 Units divided among 5 muscles (gastrocnemius, soleus, tibialis posterior, flexor hallucis longus and flexor digitorum longus) (see Table 5 and Figure 3).

Table 5: BOTOX Dosing by Muscle for Adult Lower Limb Spasticity
Muscle | Recommended Dose Total Dosage (Number of Sites)
Gastrocnemius medial head | 75 Units divided in 3 sites
Gastrocnemius lateral head | 75 Units divided in 3 sites
Soleus | 75 Units divided in 3 sites
Tibialis Posterior | 75 Units divided in 3 sites
Flexor hallucis longus | 50 Units divided in 2 sites
Flexor digitorum longus | 50 Units divided in 2 sites

Figure 3: Injection Sitesfor Adult Lower Limb Spasticity

2.7 Pediatric Spasticity

General

Localization of the involved muscles with techniques such as needle electromyographic guidance, nerve stimulation, or ultrasound is recommended. When treating both lower limbs or the upper and lower limbs in combination, the total dose should not exceed the lower of 10 Units/kg body weight or 340 Units, in a 3-month interval [see Boxed Warningand Warnings and Precautions (5.1,5.6)]. Additional general adult spasticity dosing information is also applicable to pediatric spasticity patients [see Dosage and Administration (2.6)].

Pediatric Upper Limb Spasticity

The recommended dose for treating pediatric upper limb spasticity is 3 Units/kg to 6 Units/kg divided among the affected muscles (see Table 6and Figure 4). The total dose of BOTOX administered per treatment session in the upper limb should not exceed 6 Units/kg or 200 Units, whichever is lower.

Table 6: BOTOX Dosing by Muscle for Pediatric Upper Limb Spasticity
Muscle | Recommended Dose and Number of Sites
Biceps Brachii | 1.5 Units/kg to 3 Units/kg divided in 4 sites
Brachialis | 1 Unit/kg to 2 Units/kg divided in 2 sites
Brachioradialis | 0.5 Units/kg to 1 Unit/kg divided in 2 sites
Flexor Carpi Radialis | 1 Unit/kg to 2 Units/kg divided in 2 sites
Flexor Carpi Ulnaris | 1 Unit/kg to 2 Units/kg divided in 2 sites
Flexor Digitorum Profundus | 0.5 Units/kg to 1 Unit/kg divided in 2 sites
Flexor Digitorum Sublimis | 0.5 Units/kg to 1 Unit/kg divided in 2 sites

Figure 4: Injection Sites for Pediatric Upper Limb Spasticity

Pediatric Lower Limb Spasticity

The recommended dose for treating pediatric lower limb spasticity is 4 Units/kg to 8 Units/kg divided among the affected muscles (see Table 7and Figure 5). The total dose of BOTOX administered per treatment session in the lower limb should not exceed 8 Units/kg or 300 Units, whichever is lower.

Table 7: BOTOX Dosing by Muscle for Pediatric Lower Limb Spasticity
Muscle | Recommended Dose Total Dosage (Number of Sites)
Gastrocnemius medial head | 1 Unit/kg to 2 Units/kg divided in 2 sites
Gastrocnemius lateral head | 1 Unit/kg to 2 Units/kg divided in 2 sites
Soleus | 1 Unit/kg to 2 Units/kg divided in 2 sites
Tibialis Posterior | 1 Unit/kg to 2 Units/kg divided in 2 sites

Figure 5: Injection Sites for Pediatric Lower Limb Spasticity

2.8 Cervical Dystonia

A double-blind, placebo-controlled study enrolled patients who had extended histories of receiving and tolerating BOTOX injections, with prior individualized adjustment of dose. The mean BOTOX dose administered to patients in this study was 236 Units (25th to 75th percentile range of 198 Units to 300 Units). The BOTOX dose was divided among the affected muscles [see Clinical Studies (14.7)].

Dosing in initial and sequential treatment sessions should be tailored to the individual patient based on the patient’s head and neck position, localization of pain, muscle hypertrophy, patient response, and adverse event history. The initial dose for a patient without prior use of BOTOX should be at a lower dose, with subsequent dosing adjusted based on individual response. Limiting the total dose injected into the sternocleidomastoid muscle to 100 Units or less may decrease the occurrence of dysphagia [see Warnings and Precautions (5.1,5.5,5.6)].

The recommended dilution is 200 Units/2 mL, 200 Units/4 mL, 100 Units/1 mL, or 100 Units/2 mL with preservative-free 0.9% Sodium Chloride Injection, USP, depending on volume and number of injection sites desired to achieve treatment objectives (see Table 1). In general, no more than 50 Units per site should be administered using a sterile needle (e.g., 25-30 gauge) of an appropriate length. Localization of the involved muscles with electromyographic guidance may be useful.

Clinical improvement generally begins within the first two weeks after injection with maximum clinical benefit at approximately six weeks post-injection. In the double-blind, placebo-controlled study most subjects were observed to have returned to pre-treatment status by 3 months post-treatment.

2.9 Primary Axillary Hyperhidrosis

The recommended dose is 50 Units per axilla. The hyperhidrotic area to be injected should be defined using standard staining techniques, e.g., Minor’s Iodine-Starch Test. The recommended dilution is 100 Units/4 mL with preservative-free 0.9% Sodium Chloride Injection, USP (see Table 1). Using a sterile 30 gauge needle, 50 Units of BOTOX (2 mL) is injected intradermally in 0.1 to 0.2 mL aliquots to each axilla evenly distributed in multiple sites (10-15) approximately 1-2 cm apart.

Repeat injections for hyperhidrosis should be administered when the clinical effect of a previous injection diminishes.

Instructions for the Minor’s Iodine-Starch Test Procedure:

Patients should shave underarms and abstain from use of over-the-counter deodorants or antiperspirants for 24 hours prior to the test. Patient should be resting comfortably without exercise or hot drinks for approximately 30 minutes prior to the test. Dry the underarm area and then immediately paint it with iodine solution. Allow the area to dry, then lightly sprinkle the area with starch powder. Gently blow off any excess starch powder. The hyperhidrotic area will develop a deep blue-black color over approximately 10 minutes.

Each injection site has a ring of effect of up to approximately 2 cm in diameter. To minimize the area of no effect, the injection sites should be evenly spaced as shown in Figure 6.

Figure 6: Injection Pattern for Primary Axillary Hyperhidrosis

Each dose is injected to a depth of approximately 2 mm and at a 45° angle to the skin surface, with the bevel side up to minimize leakage and to ensure the injections remain intradermal. If injection sites are marked in ink, do not inject BOTOX directly through the ink mark to avoid a permanent tattoo effect.

2.10 Blepharospasm

For blepharospasm, reconstituted BOTOX is injected using a sterile, 27-30 gauge needle without electromyographic guidance. The initial recommended dose is 1.25 Units-2.5 Units (0.05 mL to 0.1 mL volume at each site) injected into the medial and lateral pre-tarsal orbicularis oculi of the upper lid and into the lateral pre-tarsal orbicularis oculi of the lower lid. Avoiding injection near the levator palpebrae superioris may reduce the complication of ptosis. Avoiding medial lower lid injections, and thereby reducing diffusion into the inferior oblique, may reduce the complication of diplopia. Ecchymosis occurs easily in the soft eyelid tissues. This can be prevented by applying pressure at the injection site immediately after the injection.

The recommended dilution to achieve 1.25 Units is 100 Units/8 mL; for 2.5 Units it is 100 Units/4 mL (see Table 1).

In general, the initial effect of the injections is seen within three days and reaches a peak at one to two weeks post-treatment. Each treatment lasts approximately three months, following which the procedure can be repeated. At repeat treatment sessions, the dose may be increased up to two-fold if the response from the initial treatment is considered insufficient, usually defined as an effect that does not last longer than two months. However, there appears to be little benefit obtainable from injecting more than 5 Units per site. Some tolerance may be found when BOTOX is used in treating blepharospasm if treatments are given any more frequently than every three months, and is rare to have the effect be permanent.

The cumulative dose of BOTOX treatment for blepharospasm in a 30-day period should not exceed 200 Units.

2.11 Strabismus

BOTOX is intended for injection into extraocular muscles utilizing the electrical activity recorded from the tip of the injection needle as a guide to placement within the target muscle. Injection without surgical exposure or electromyographic guidance should not be attempted. Physicians should be familiar with electromyographic technique.

To prepare the eye for BOTOX injection, it is recommended that several drops of a local anesthetic and an ocular decongestant be given several minutes prior to injection.

The volume of BOTOX injected for treatment of strabismus should be between 0.05-0.15 mL per muscle.

The initial listed doses of the reconstituted BOTOX [see Dosage and Administration (2.2)]typically create paralysis of the injected muscles beginning one to two days after injection and increasing in intensity during the first week. The paralysis lasts for 2-6 weeks and gradually resolves over a similar time period. Overcorrections lasting over six months have been rare. About one half of patients will require subsequent doses because of inadequate paralytic response of the muscle to the initial dose, or because of mechanical factors such as large deviations or restrictions, or because of the lack of binocular motor fusion to stabilize the alignment.

Initial Doses in Units

Use the lower listed doses for treatment of small deviations. Use the larger doses only for large deviations.

- For vertical muscles, and for horizontal strabismus of less than 20 prism diopters: 1.25 Units-2.5 Units in any one muscle.
- For horizontal strabismus of 20 prism diopters to 50 prism diopters: 2.5 Units-5 Units in any one muscle.
- For persistent VI nerve palsy of one month or longer duration: 1.25 Units-2.5 Units in the medial rectus muscle.

Subsequent Doses for Residual or Recurrent Strabismus

- It is recommended that patients be re-examined 7-14 days after each injection to assess the effect of that dose.
- Patients experiencing adequate paralysis of the target muscle that require subsequent injections should receive a dose comparable to the initial dose.
- Subsequent doses for patients experiencing incomplete paralysis of the target muscle may be increased up to two-fold compared to the previously administered dose.
- Subsequent injections should not be administered until the effects of the previous dose have dissipated as evidenced by substantial function in the injected and adjacent muscles.
- The maximum recommended dose as a single injection for any one muscle is 25 Units.

The recommended dilution to achieve 1.25 Units is 100 Units/8 mL; for 2.5 Units it is 100 Units/4 mL (see Table 1).

3 DOSAGE FORMS AND STRENGTHS

For Injection: sterile 100 Units Units vacuum-dried powder in single-dose vials for reconstitution only with sterile, preservative-free 0.9% Sodium Chloride Injection, USP prior to injection.

4 CONTRAINDICATIONS

BOTOX is contraindicated:

- In patients who are hypersensitive to any botulinum toxin product or to any of the components in the formulation [see Warnings and Precautions (5.4)].
- In the presence of infection at the proposed injection site(s).
- For intradetrusor injection in patients with a urinary tract infection; or in patients with urinary retention or post-void residual (PVR) urine volume >200 mL who are not routinely performing clean intermittent self-catheterization (CIC) [see Warnings and Precautions (5.12,5.13)].

5 WARNINGS AND PRECAUTIONS

5.1 Spread of Toxin Effect

Postmarketing safety data from BOTOX and other approved botulinum toxins suggest that botulinum toxin effects may, in some cases, be observed beyond the site of local injection. The symptoms are consistent with the mechanism of action of botulinum toxin and may include asthenia, generalized muscle weakness, diplopia, ptosis, dysphagia, dysphonia, dysarthria, urinary incontinence, and breathing difficulties. These symptoms have been reported hours to weeks after injection. Swallowing and breathing difficulties can be life threatening and there have been reports of death related to spread of toxin effects. The risk of symptoms is probably greatest in children treated for spasticity but symptoms can also occur in adults treated for spasticity and other conditions, and particularly in those patients who have an underlying condition that would predispose them to these symptoms. In unapproved uses and in approved indications, symptoms consistent with spread of toxin effect have been reported at doses comparable to or lower than doses used to treat cervical dystonia and spasticity. Patients or caregivers should be advised to seek immediate medical care if swallowing, speech or respiratory disorders occur.

No definitive serious adverse event reports of distant spread of toxin effect associated with BOTOX for blepharospasm at the recommended dose (30 Units and below), severe primary axillary hyperhidrosis at the recommended dose (100 Units), strabismus, or for chronic migraine at the labeled doses have been reported.

5.2 Lack of Interchangeability between Botulinum Toxin Products

The potency Units of BOTOX are specific to the preparation and assay method utilized. They are not interchangeable with other preparations of botulinum toxin products and, therefore, units of biological activity of BOTOX cannot be compared to nor converted into units of any other botulinum toxin products assessed with any other specific assay method [see Description (11)].

5.3 Serious Adverse Reactions with Unapproved Use

Serious adverse reactions, including excessive weakness, dysphagia, and aspiration pneumonia, with some adverse reactions associated with fatal outcomes, have been reported in patients who received BOTOX injections for unapproved uses. In these cases, the adverse reactions were not necessarily related to distant spread of toxin, but may have resulted from the administration of BOTOX to the site of injection and/or adjacent structures. In several of the cases, patients had pre-existing dysphagia or other significant disabilities. There is insufficient information to identify factors associated with an increased risk for adverse reactions associated with the unapproved uses of BOTOX. The safety and effectiveness of BOTOX for unapproved uses have not been established.

5.4 Hypersensitivity Reactions

Serious and/or immediate hypersensitivity reactions have been reported. These reactions include anaphylaxis, serum sickness, urticaria, soft tissue edema, and dyspnea. If such a reaction occurs, further injection of BOTOX should be discontinued and appropriate medical therapy immediately instituted. One fatal case of anaphylaxis has been reported in which lidocaine was used as the diluent, and consequently the causal agent cannot be reliably determined.

5.5 Increased Risk of Clinically Significant Effects with Pre-Existing Neuromuscular Disorders

Individuals with peripheral motor neuropathic diseases, amyotrophic lateral sclerosis or neuromuscular junction disorders (e.g., myasthenia gravis or Lambert-Eaton syndrome) should be monitored when given botulinum toxin. Patients with known or unrecognized neuromuscular disorders or neuromuscular junction disorders may be at increased risk of clinically significant effects including generalized muscle weakness, diplopia, ptosis, dysphonia, dysarthria, severe dysphagia and respiratory compromise from therapeutic doses of BOTOX [see Warnings and Precautions (5.1,5.6)].

5.6 Dysphagia and Breathing Difficulties

Treatment with BOTOX and other botulinum toxin products can result in swallowing or breathing difficulties. Patients with pre-existing swallowing or breathing difficulties may be more susceptible to these complications. In most cases, this is a consequence of weakening of muscles in the area of injection that are involved in breathing or oropharyngeal muscles that control swallowing or breathing [see Warnings and Precautions (5.1)].

Deaths as a complication of severe dysphagia have been reported after treatment with botulinum toxin. Dysphagia may persist for several months, and require use of a feeding tube to maintain adequate nutrition and hydration. Aspiration may result from severe dysphagia and is a particular risk when treating patients in whom swallowing or respiratory function is already compromised.

Treatment with botulinum toxins may weaken neck muscles that serve as accessory muscles of ventilation. This may result in a critical loss of breathing capacity in patients with respiratory disorders who may have become dependent upon these accessory muscles. There have been postmarketing reports of serious breathing difficulties, including respiratory failure.

Patients with smaller neck muscle mass and patients who require bilateral injections into the sternocleidomastoid muscle for the treatment of cervical dystonia have been reported to be at greater risk for dysphagia. Limiting the dose injected into the sternocleidomastoid muscle may reduce the occurrence of dysphagia. Injections into the levator scapulae may be associated with an increased risk of upper respiratory infection and dysphagia.

Patients treated with botulinum toxin may require immediate medical attention should they develop problems with swallowing, speech or respiratory disorders. These reactions can occur within hours to weeks after injection with botulinum toxin [see Warnings and Precautions (5.1)].

5.7 Pulmonary Effects of BOTOX in Patients with Compromised Respiratory Status Treated for Spasticity or for Detrusor Overactivity Associatedwith a Neurologic Condition

Patients with compromised respiratory status treated with BOTOX for spasticity should be monitored closely. In a double-blind, placebo-controlled, parallel group study in adult patients treated for upper limb spasticity with stable reduced pulmonary function (defined as FEV140-80% of predicted value and FEV1/FVC ≤ 0.75), the event rate in change of Forced Vital Capacity (FVC) ≥15% or ≥20% was generally greater in patients treated with BOTOX than in patients treated with placebo (see Table 8).

Table 8: Event Rate Per Patient Treatment Cycle Among Adult Upper Limb Spasticity Patients with Reduced Lung Function Who Experienced at Least a 15% or 20% Decrease in FVC From Baseline at Week 1, 6, 12 Post-injection with Up to Two Treatment Cycles with BOTOX or Placebo
 | BOTOX 360 Units |  | BOTOX 240 Units |  | Placebo
 | ≥15% | ≥20% | ≥15% | ≥20% | ≥15% | ≥20%
Week 1 | 4% | 0% | 3% | 0% | 7% | 3%
Week 6 | 7% | 4% | 4% | 2% | 2% | 2%
Week 12 | 10% | 5% | 2% | 1% | 4% | 1%

Differences from placebo were not statistically significant

In adult spasticity patients with reduced lung function, upper respiratory tract infections were also reported more frequently as adverse reactions in patients treated with BOTOX than in patients treated with placebo [see Warnings and Precautions (5.10)].

In a double-blind, placebo-controlled, parallel group study in adult patients with detrusor overactivity associated with a neurologic condition and restrictive lung disease of neuromuscular etiology [defined as FVC 50-80% of predicted value in patients with spinal cord injury between C5 and C8, or MS] the event rate in change of Forced Vital Capacity ≥15% or ≥20% was generally greater in patients treated with BOTOX than in patients treated with placebo (see Table 9).

Table 9: Number and Percent of Patients Experiencing at Least a 15% or 20% Decrease in FVC From Baseline at Week 2, 6, 12 Post-Injection with BOTOX or Placebo
 | BOTOX 200 Units |  | Placebo
 | ≥15% | ≥20% | ≥15% | ≥20%
Week 2 | 0/15 (0%) | 0/15 (0%) | 1/11 (9%) | 0/11 (0%)
Week 6 | 2/13 (15%) | 1/13 (8%) | 0/12 (0%) | 0/12 (0%)
Week 12 | 0/12(0%) | 0/12 (0%) | 0/7 (0%) | 0/7 (0%)

5.8 Corneal Exposure and Ulceration in Patients Treated with BOTOX for Blepharospasm

Reduced blinking from BOTOX injection of the orbicularis muscle can lead to corneal exposure, persistent epithelial defect, and corneal ulceration, especially in patients with VII nerve disorders. Vigorous treatment of any epithelial defect should be employed. This may require protective drops, ointment, therapeutic soft contact lenses, or closure of the eye by patching or other means.

5.9 Retrobulbar Hemorrhages in Patients Treated with BOTOX for Strabismus

During the administration of BOTOX for the treatment of strabismus, retrobulbar hemorrhages sufficient to compromise retinal circulation have occurred. It is recommended that appropriate instruments to decompress the orbit be accessible.

5.10 Bronchitis and Upper Respiratory Tract Infections in Patients Treated for Spasticity

Bronchitis was reported more frequently as an adverse reaction in adult patients treated for upper limb spasticity with BOTOX (3% at 251 Units-360 Units total dose), compared to placebo (1%). In adult patients with reduced lung function treated for upper limb spasticity, upper respiratory tract infections were also reported more frequently as adverse reactions in patients treated with BOTOX (11% at 360 Units total dose; 8% at 240 Units total dose) compared to placebo (6%). In adult patients treated for lower limb spasticity, upper respiratory tract infections were reported more frequently as an adverse reaction in patients treated with BOTOX (2% at 300 Units to 400 Units total dose) compared to placebo (1%). In pediatric patients treated for upper limb spasticity, upper respiratory tract infections were reported more frequently as an adverse reaction in patients treated with BOTOX (17% at 6 Units/kg and 10% at 3 Units/kg) compared to placebo (9%). In pediatric patients treated for lower limb spasticity, upper respiratory tract infection was not reported with an incidence greater than placebo.

5.11 Autonomic Dysreflexia in Patients Treated for Detrusor Overactivity Associatedwith a Neurologic Condition

Autonomic dysreflexia associated with intradetrusor injections of BOTOX could occur in patients treated for detrusor overactivity associated with a neurologic condition and may require prompt medical therapy. In clinical trials, the incidence of autonomic dysreflexia was greater in adult patients treated with BOTOX 200 Units compared with placebo (1.5% versus 0.4%, respectively).

5.12 Urinary Tract Infections in Patients with Overactive Bladder

BOTOX increases the incidence of urinary tract infection [see Adverse Reactions (6.1)]. Clinical trials for overactive bladder excluded patients with more than 2 UTIs in the past 6 months and those taking antibiotics chronically due to recurrent UTIs. Use of BOTOX for the treatment of overactive bladder in such patients and in patients with multiple recurrent UTIs during treatment should only be considered when the benefit is likely to outweigh the potential risk.

5.13 Urinary Retention in Adults Treated for Bladder Dysfunction

Due to the risk of urinary retention, treat only patients who are willing and able to initiate catheterization post-treatment, if required, for urinary retention.

In patients who are not catheterizing, post-void residual (PVR) urine volume should be assessed within 2 weeks post-treatment and periodically as medically appropriate up to 12 weeks, particularly in patients with multiple sclerosis or diabetes mellitus. Depending on patient symptoms, institute catheterization if PVR urine volume exceeds 200 mL and continue until PVR falls below 200 mL. Instruct patients to contact their physician if they experience difficulty in voiding as catheterization may be required.

The incidence and duration of urinary retention is described below for adult patients with overactive bladder and detrusor overactivity associated with a neurologic condition who received BOTOX or placebo injections.

Overactive Bladder

In double-blind, placebo-controlled trials in patients with OAB, the proportion of subjects who initiated clean intermittent catheterization (CIC) for urinary retention following treatment with BOTOX or placebo is shown in Table 10. The duration of post-injection catheterization for those who developed urinary retention is also shown.

Table 10: Proportion of Patients Catheterizing for Urinary Retention and Duration of Catheterization Following an Injection in Double-Blind, Placebo-Controlled Clinical Trials in OAB
Timepoint | BOTOX 100 Units (N=552) | Placebo (N=542)
Proportion of Patients Catheterizing for Urinary Retention
At any time during complete treatment cycle | 6.5% (n=36) | 0.4% (n=2)
Duration of Catheterization for Urinary Retention (Days)
Median | 63 | 11
Min, Max | 1, 214 | 3, 18

Patients with diabetes mellitus treated with BOTOX were more likely to develop urinary retention than those without diabetes, as shown in Table 11.

Table 11: Proportion of Patients Experiencing Urinary Retention Following an Injection in Double-Blind, Placebo-Controlled Clinical Trials in OAB According to History of Diabetes Mellitus
 | Patients with Diabetes |  | Patients without Diabetes
 | BOTOX 100 Units (N=81) | Placebo (N=69) | BOTOX 100 Units (N=526) | Placebo (N=516)
Urinary retention | 12.3% (n=10) | 0 | 6.3% (n=33) | 0.6% (n=3)

Adult Detrusor Overactivity associated with a Neurologic Condition

In two double-blind, placebo-controlled trials in adult patients with detrusor overactivity associated with a neurologic condition (NDO-1 and NDO-2), the proportion of subjects who were not using clean intermittent catheterization (CIC) prior to injection and who subsequently required catheterization for urinary retention following treatment with BOTOX 200 Units or placebo is shown in Table 12. The duration of post-injection catheterization for those who developed urinary retention is also shown.

Table 12: Proportion of Adult Patients Not Using CIC at Baseline and then Catheterizing for Urinary Retention and Duration of Catheterization Following an Injection in Double-Blind, Placebo-Controlled Clinical Trials
Timepoint | BOTOX 200 Units (N=108) | Placebo (N=104)
Proportion of Patients Catheterizing for Urinary Retention
At any time during complete treatment cycle | 30.6% (n=33) | 6.7% (n=7)
Duration of Catheterization for Urinary Retention (Days)
Median | 289 | 358
Min, Max | 1, 530 | 2, 379

Among adult patients not using CIC at baseline, those with Multiple Sclerosis (MS) were more likely to require CIC post-injection than those with Spinal Cord Injury (SCI) (see Table 13).

Table 13: Proportion of Adult Patients by Etiology (MS and SCI) Not Using CIC at Baseline and then Catheterizing for Urinary Retention Following an Injection in Double-Blind, Placebo-Controlled Clinical Trials
Timepoint | MS |  | SCI
 | BOTOX 200 Units (N=86) | Placebo (N=88) | BOTOX 200 Units (N=22) | Placebo (N=16)
At any time during complete treatment cycle | 31% (n=27) | 5% (n=4) | 27% (n=6) | 19% (n=3)

A placebo-controlled, double-blind post-approval 52 week study with BOTOX 100 Units (Study NDO-3) was conducted in non-catheterizing adult MS patients with urinary incontinence due to detrusor overactivity associated with a neurologic condition. Catheterization for urinary retention was initiated in 15.2% (10/66) of patients following treatment with BOTOX 100 Units versus 2.6% (2/78) on placebo at any time during the complete treatment cycle. The median duration of post-injection catheterization for those who developed urinary retention was 64 days for BOTOX 100 Units and 2 days for placebo.

5.14 Human Albumin and Transmission of Viral Diseases

This product contains albumin, a derivative of human blood. Based on effective donor screening and product manufacturing processes, it carries an extremely remote risk for transmission of viral diseases and variant Creutzfeldt-Jakob disease (vCJD). There is a theoretical risk for transmission of Creutzfeldt-Jakob disease (CJD), but if that risk actually exists, the risk of transmission would also be considered extremely remote. No cases of transmission of viral diseases, CJD or vCJD have ever been identified for licensed albumin or albumin contained in other licensed products.

6 ADVERSE REACTIONS

The following adverse reactions to BOTOX (onabotulinumtoxinA) for injection are discussed in greater detail in other sections of the labeling:

- Spread of Toxin Effects [see Warnings and Precautions (5.1)]
- Serious Adverse Reactions with Unapproved Use [see Warnings and Precautions (5.3)]
- Hypersensitivity Reactions [see Contraindications (4) and Warnings and Precautions (5.4)]
- Increased Risk of Clinically Significant Effects with Pre-Existing Neuromuscular Disorders [see Warnings and Precautions (5.5)]
- Dysphagia and Breathing Difficulties [see Warningsand Precautions (5.6)]
- Pulmonary Effects of BOTOX in Patients with Compromised Respiratory Status Treated for Spasticity or for Detrusor Overactivity Associated with a Neurologic Condition [see Warnings and Precautions (5.7)]
- Corneal Exposure and Ulceration in Patients Treated with BOTOX for Blepharospasm [see Warnings and Precautions (5.8)]
- Retrobulbar Hemorrhages in Patients Treated with BOTOX for Strabismus [see Warnings and Precautions (5.9)]
- Bronchitis and Upper Respiratory Tract Infections in Patients Treated for Spasticity [see Warnings and Precautions (5.10)]
- Autonomic Dysreflexia in Patients Treated for Detrusor Overactivity Associated with a Neurologic Condition [see Warnings and Precautions (5.11)]
- Urinary Tract Infections in Patients with Overactive Bladder [see Warnings and Precautions (5.12)]
- Urinary Retention in Patients Treated for Bladder Dysfunction [see Warnings and Precautions (5.13)]

6.1 Clinical Trials Experience

Because clinical trials are conducted under widely varying conditions, the adverse reaction rates observed in the clinical trials of a drug cannot be directly compared to rates in the clinical trials of another drug and may not reflect the rates observed in clinical practice.

BOTOX and BOTOX Cosmetic contain the same active ingredient in the same formulation, but with different labeled Indications and Usage. Therefore, adverse reactions observed with the use of BOTOX Cosmetic also have the potential to be observed with the use of BOTOX.

In general, adverse reactions occur within the first week following injection of BOTOX and, while generally transient, may have a duration of several months or longer. Localized pain, infection, inflammation, tenderness, swelling, erythema, and/or bleeding/bruising may be associated with the injection. Symptoms associated with flu-like symptoms (e.g., nausea, fever, myalgia) have been reported after treatment. Needle-related pain and/or anxiety may result in vasovagal responses (including syncope, hypotension), which may require appropriate medical therapy.

Local weakness of the injected muscle(s) represents the expected pharmacological action of botulinum toxin. However, weakness of nearby muscles may also occur due to spread of toxin [see Warnings and Precautions (5.1)].

Overactive Bladder

Table 14 presents the most frequently reported adverse reactions in double-blind, placebo-controlled clinical trials for overactive bladder occurring within 12 weeks of the first BOTOX treatment.

Table 14: Adverse Reactions Reported by ≥2% of BOTOX Treated Patients and More Often than in Placebo-Treated Patients Within the First 12 Weeks after Intradetrusor Injection, in Double-Blind, Placebo-Controlled Clinical Trials in Patients with OAB
Adverse Reactions | BOTOX 100 Units (N=552) % | Placebo (N=542) %
Urinary tract infection Dysuria Urinary retention Bacteriuria Residual urine volume* | 18 9 6 4 3 | 6 7 0 2 0

*Elevated PVR not requiring catheterization. Catheterization was required for PVR ≥350 mL regardless of symptoms, and for PVR ≥200 mL to <350 mL with symptoms (e.g., voiding difficulty).

A higher incidence of urinary tract infection was observed in patients with diabetes mellitus treated with BOTOX 100 Units and placebo than in patients without diabetes, as shown in Table 15.

Table 15: Proportion of Patients Experiencing Urinary Tract Infection Following an Injection in Double-Blind, Placebo-Controlled Clinical Trials in OAB According to History of Diabetes Mellitus
 | Patients with Diabetes |  | Patients without Diabetes
 | BOTOX 100 Units (N=81) % | Placebo (N=69) % | BOTOX 100 Units (N=526) % | Placebo (N=516) %
Urinary tract infection (UTI) | 31 | 12 | 26 | 10

The incidence of UTI increased in patients who experienced a maximum post-void residual (PVR) urine volume ≥200 mL following BOTOX injection compared to those with a maximum PVR <200 mL following BOTOX injection, 44% versus 23%, respectively.

No change was observed in the overall safety profile with repeat dosing during an open-label, uncontrolled extension trial.

Adult Detrusor Overactivity associated with a Neurologic Condition

Table 16 presents the most frequently reported adverse reactions in the double-blind, placebo-controlled studies within 12 weeks of injection for patients with detrusor overactivity associated with a neurologic condition treated with BOTOX 200 Units.

Table 16: Adverse Reactions Reported by ≥2% of BOTOX-Treated Patients and More Frequent than in Placebo-Treated Patients Within the First 12 Weeks after Intradetrusor Injection in Double-Blind, Placebo-Controlled Clinical Trials
Adverse Reactions | BOTOX 200 Units (N=262) % | Placebo (N=272) %
Urinary tract infection Urinary retention Hematuria | 24 17 4 | 17 3 3

The following adverse reactions with BOTOX 200 Units were reported at any time following initial injection and prior to re-injection or study exit (median duration of exposure was 44 weeks): urinary tract infections (49%), urinary retention (17%), constipation (4%), muscular weakness (4%), dysuria (4%), fall (3%), gait disturbance (3%), and muscle spasm (2%).

In the Multiple Sclerosis (MS) patients enrolled in the double-blind, placebo-controlled trials, the MS exacerbation annualized rate (i.e., number of MS exacerbation events per patient-year) was 0.23 for BOTOX and 0.20 for placebo.

No change was observed in the overall safety profile with repeat dosing.

Table 17 presents the most frequently reported adverse reactions in a placebo-controlled, double-blind post-approval 52 week study with BOTOX 100 Units (Study NDO-3) conducted in MS patients with urinary incontinence due to detrusor overactivity associated with a neurologic condition. These patients were not adequately managed with at least one anticholinergic agent and not catheterized at baseline. The table below presents the most frequently reported adverse reactions within 12 weeks of injection.

Table 17: Adverse Reactions Reported in a Post Approval Study (NDO-3) by >2% of BOTOX Treated Patients and More Frequent than in Placebo-Treated Patients Within the First 12 Weeks after Intradetrusor Injection
Adverse Reactions | BOTOX 100 Units (N=66) % | Placebo (N=78) %
Urinary tract infection Bacteriuria Urinary retention Dysuria Residual urine volume* | 26 9 15 5 17 | 6 5 1 1 1

* Elevated PVR not requiring catheterization. Catheterization was required for PVR ≥350 mL regardless of symptoms, and for PVR ≥200 mL to <350 mL with symptoms (e.g., voiding difficulty).

The following adverse events with BOTOX 100 Units were reported at any time following initial injection and prior to re-injection or study exit (median duration of exposure was 51 weeks): urinary tract infections (39%), bacteriuria (18%), urinary retention (17%), residual urine volume* (17%), dysuria (9%), and hematuria (5%).

No difference in the MS exacerbation annualized rate (i.e., number of MS exacerbating events per patient-year) was observed (BOTOX =0, placebo =0.07).

Pediatric Detrusor Overactivity associated with a Neurologic Condition

Table 18 presents the most frequently reported adverse reactions in Study 191622-120, a double-blind, parallel-group study conducted in pediatric patients with detrusor overactivity associated with a neurologic condition. These patients were not adequately managed with at least one anticholinergic agent and were using clean intermittent catheterization at baseline [see Clinical Studies (14.3)].The table below presents the most frequently reported adverse reactions during the 12 weeks following intradetrusor administration of BOTOX 200 Units.

Table 18: Adverse Reactions Reported by ≥ 3% of BOTOX Treated Pediatric Patients within the First 12 Weeks after Intradetrusor Injection, Study 191622-120
Adverse Reactions | BOTOX 200 Unit (N=30)
Urinary tract infection | 2 (7%)
Bacteriuria | 6 (20%)
Leukocyturia | 2 (7%)
Hematuria | 1 (3%)

No change was observed in the overall safety profile with repeat dosing.

The most common adverse reactions in patients who received BOTOX 6 U/kg and less than a total dose of 200 U in Study 191622-120 were urinary tract infection (UTI), bacteriuria and hematuria.

Chronic Migraine

In double-blind, placebo-controlled chronic migraine efficacy trials (Study 1 and Study 2), the discontinuation rate was 12% in the BOTOX treated group and 10% in the placebo-treated group. Discontinuations due to an adverse event were 4% in the BOTOX group and 1% in the placebo group. The most frequent adverse events leading to discontinuation in the BOTOX group were neck pain, headache, worsening migraine, muscular weakness and eyelid ptosis.

The most frequently reported adverse reactions following injection of BOTOX for chronic migraine appear in Table 19.

Table 19: Adverse Reactions Reported by ≥2% of BOTOX Treated Patients and More Frequent than in Placebo-Treated Patients in Two Chronic Migraine Double-Blind, Placebo-Controlled Clinical Trials
Adverse Reactions | BOTOX 155 Units-195 Units (N=687) % |  | Placebo (N=692) %
Nervous system disorders Headache Migraine Facial paresis | 5 4 2 |  | 3 3 0
Eye disorders Eyelid ptosis | 4 |  | <1
Infections and Infestations Bronchitis | 3 |  | 2
Musculoskeletal and connective tissue disorders Neck pain Musculoskeletal stiffness Muscular weakness Myalgia Musculoskeletal pain Muscle spasms | 9 4 4 3 3 2 |  | 3 1 <1 1 1 1
General disorders and administration site conditions Injection site pain | 3 |  | 2
Vascular Disorders Hypertension | 2 |  | 1

Other adverse reactions that occurred more frequently in the BOTOX group compared to the placebo group at a frequency less than 1% and potentially BOTOX related include: vertigo, dry eye, eyelid edema, dysphagia, eye infection, and jaw pain. Severe worsening of migraine requiring hospitalization occurred in approximately 1% of BOTOX treated patients in Study 1 and Study 2, usually within the first week after treatment, compared to 0.3% of placebo-treated patients.

Adult Upper Limb Spasticity

The most frequently reported adverse reactions following injection of BOTOX for adult upper limb spasticity appear in Table 20.

Table 20: Adverse Reactions Reported by ≥2% of BOTOX Treated Patients and More Frequent than in Placebo-Treated Patients in Adult Upper Limb Spasticity Double-Blind, Placebo-Controlled Clinical Trials
Adverse Reactions | BOTOX 251 Units- 360 Units (N=115) % | BOTOX 150 Units- 250 Units (N=188) % | BOTOX <150 Units (N=54) % | Placebo (N=182) %
Gastrointestinal disorder Nausea | 3 | 2 | 2 | 1
General disorders and administration site conditions Fatigue | 3 | 2 | 2 | 0
Infections and infestations Bronchitis | 3 | 2 | 0 | 1
Musculoskeletal and connective tissue disorders Pain in extremity Muscular weakness | 6 0 | 5 4 | 9 2 | 4 1

Twenty-two adult patients, enrolled in double-blind placebo controlled studies, received 400 Units or higher of BOTOX for treatment of upper limb spasticity. In addition, 44 adults received 400 Units of BOTOX or higher for four consecutive treatments over approximately one year for treatment of upper limb spasticity. The type and frequency of adverse reactions observed in patients treated with 400 Units of BOTOX were similar to those reported in patients treated for upper limb spasticity with 360 Units of BOTOX.

Adult Lower LimbSpasticity

The most frequently reported adverse reactions following injection of BOTOX for adult lower limb spasticity appear in Table 21. Two hundred thirty-one patients enrolled in a double-blind placebo controlled study (Study 7) received 300 Units to 400 Units of BOTOX, and were compared with 233 patients who received placebo. Patients were followed for an average of 91 days after injection.

Table 21: Adverse Reactions Reported by ≥2% of BOTOX Treated Patients and More Frequent than in Placebo-Treated Patients in Adult Lower Limb Spasticity Double-Blind, Placebo-Controlled Clinical Trial (Study 7)
Adverse Reactions | BOTOX (N=231) % | Placebo (N=233) %
Musculoskeletal and connective tissue disorders Arthralgia Back pain Myalgia | 3 3 2 | 1 2 1
Infections and infestations Upper respiratory tract infection | 2 | 1
General disorders and administration site conditions Injection site pain | 2 | 1

Pediatric Upper Limb Spasticity

The most frequently reported adverse reactions following injection of BOTOX in pediatric patients 2 to 17 years of age with upper limb spasticity appear in Table 22. In a double-blind, placebo-controlled trial (Study 1), 78 patients were treated with 3 Units/kg of BOTOX, and 77 patients received 6 Units/kg to a maximum dose of 200 Units of BOTOX, and were compared to 79 patients who received placebo [see Clinical Studies (14.6)].Patients were followed for an average of 91 days after injection.

Table 22: Adverse Reactions Reported by ≥2% of BOTOX 6 Units/kg Treated Patients and More Frequent than in Placebo-Treated Patients in Pediatric Upper Limb Spasticity Double-Blind, Placebo-Controlled Clinical Trial (Study 1)
Adverse Reactions | BOTOX 6 Units/kg (N=77) % | BOTOX 3 Units/kg (N=78) % | Placebo (N=79) %
Infections and infestations Upper respiratory tract infection* | 17 | 10 | 9
General disorders and administration site conditions Injection site pain | 4 | 3 | 1
Gastrointestinal disorders Nausea Constipation | 4 3 | 0 0 | 0 1
Respiratory, thoracic and mediastinal disorders Rhinorrhea Nasal congestion | 4 3 | 0 0 | 1 1
Nervous system disorders Seizure** | 5 | 1 | 0

*Includes upper respiratory tract infection and viral upper respiratory tract infection

**Includes seizure and partial seizure

Pediatric Lower Limb Spasticity

The most frequently reported adverse reactions following injection of BOTOX in pediatric patients 2 to 17 years of age with lower limb spasticity appear in Table 23. In a double-blind, placebo-controlled trial (Study 2), 126 patients were treated with 4 Units/kg of BOTOX, and 128 patients received 8 Units/kg to a maximum dose of 300 Units of BOTOX, and were compared to 128 patients who received placebo [see Clinical Studies (14.6)]. Patients were followed for an average of 89 days after injection.

Table 23: Adverse Reactions Reported by ≥2% of BOTOX 8 Units/kg Treated Patients and More Frequent than in Placebo-Treated Patients in Pediatric Lower Limb Spasticity Double-Blind, Placebo-Controlled Clinical Trial (Study 2)
Adverse Reactions | BOTOX 8 Units/kg (N=128) % | BOTOX 4 Units/kg (N=126) % | Placebo (N=128) %
General disorders and administration site conditions Injection site erythema Injection site pain | 2 2 | 0 2 | 0 0
Respiratory, thoracic and mediastinal disorders Oropharyngeal pain | 2 | 0 | 1
Injury, poisoning and procedural complications Ligament sprain Skin abrasion | 2 2 | 1 0 | 0 0
Metabolism and nutrition disorders Decreased appetite | 2 | 0 | 0

Cervical Dystonia

In cervical dystonia patients evaluated for safety in double-blind and open-label studies following injection of BOTOX, the most frequently reported adverse reactions were dysphagia (19%), upper respiratory infection (12%), neck pain (11%), and headache (11%).

Other events reported in 2-10% of patients in any one study in decreasing order of incidence include: increased cough, flu syndrome, back pain, rhinitis, dizziness, hypertonia, soreness at injection site, asthenia, oral dryness, speech disorder, fever, nausea, and drowsiness. Stiffness, numbness, diplopia, ptosis, and dyspnea have been reported.

Dysphagia and symptomatic general weakness may be attributable to an extension of the pharmacology of BOTOX resulting from the spread of the toxin outside the injected muscles [see Warnings and Precautions (5.1,5.6)].

The most common severe adverse reaction associated with the use of BOTOX injection in patients with cervical dystonia is dysphagia with about 20% of these cases also reporting dyspnea [see Warnings and Precautions (5.1,5.6)]. Most dysphagia is reported as mild or moderate in severity. However, it may be associated with more severe signs and symptoms [see Warnings and Precautions (5.6)].

Additionally, reports in the literature include a case of a female patient who developed brachial plexopathy two days after injection of 120 Units of BOTOX for the treatment of cervical dystonia, and reports of dysphonia in patients who have been treated for cervical dystonia.

Primary Axillary Hyperhidrosis

The most frequently reported adverse reactions (3-10% of adult patients) following injection of BOTOX in double-blind studies included injection site pain and hemorrhage, non-axillary sweating, infection, pharyngitis, flu syndrome, headache, fever, neck or back pain, pruritus, and anxiety.

The data reflect 346 patients exposed to BOTOX 50 Units and 110 patients exposed to BOTOX 75 Units in each axilla.

Blepharospasm

In a study of blepharospasm patients who received an average dose per eye of 33 Units (injected at 3 to 5 sites) of the currently manufactured BOTOX, the most frequently reported adverse reactions were ptosis (21%), superficial punctate keratitis (6%), and eye dryness (6%).

Other events reported in prior clinical studies in decreasing order of incidence include: irritation, tearing, lagophthalmos, photophobia, ectropion, keratitis, diplopia, entropion, diffuse skin rash, and local swelling of the eyelid skin lasting for several days following eyelid injection.

In two cases of VII nerve disorder, reduced blinking from BOTOX injection of the orbicularis muscle led to serious corneal exposure, persistent epithelial defect, corneal ulceration and a case of corneal perforation. Focal facial paralysis, syncope, and exacerbation of myasthenia gravis have also been reported after treatment of blepharospasm.

Strabismus

Extraocular muscles adjacent to the injection site can be affected, causing vertical deviation, especially with higher doses of BOTOX. The incidence rates of these adverse effects in 2058 adults who received a total of 3650 injections for horizontal strabismus was 17%.

The incidence of ptosis has been reported to be dependent on the location of the injected muscles, 1% after inferior rectus injections, 16% after horizontal rectus injections and 38% after superior rectus injections.

In a series of 5587 injections, retrobulbar hemorrhage occurred in 0.3% of cases.

6.2 Immunogenicity

As with all therapeutic proteins, there is a potential for immunogenicity. The detection of antibody formation is highly dependent on the sensitivity and specificity of the assay. Additionally, the observed incidence of antibody (including neutralizing antibody) positivity in an assay may be influenced by several factors including assay methodology, sample handling, timing of sample collection, concomitant medications, and underlying disease. For these reasons, comparison of the incidence of antibodies to onabotulinumtoxinA in the studies described below with the incidence of antibodies in other studies or to other products may be misleading.

In a long term, open-label study evaluating 326 cervical dystonia patients treated for an average of 9 treatment sessions with the current formulation of BOTOX, 4 (1.2%) patients had positive antibody tests. All 4 of these patients responded to BOTOX therapy at the time of the positive antibody test. However, 3 of these patients developed clinical resistance after subsequent treatment, while the fourth patient continued to respond to BOTOX therapy for the remainder of the study.

One patient among the 445 hyperhidrosis patients (0.2%), two patients among the 380 adult upper limb spasticity patients (0.5%), and no patients among 406 migraine patients with analyzed specimens developed the presence of neutralizing antibodies.

In one Phase 3 study and the open-label extension study in patients with pediatric lower limb spasticity, neutralizing antibodies developed in 2 of 264 patients (0.8%) treated with BOTOX for up to 5 treatment cycles. Both patients continued to experience clinical benefit following subsequent BOTOX treatments.

In overactive bladder patients with analyzed specimens from the two phase 3 studies and the open-label extension study, neutralizing antibodies developed in 0 of 954 patients (0.0%) while receiving BOTOX 100 Unit doses and 3 of 260 patients (1.2%) after subsequently receiving at least one 150 Unit dose. Response to subsequent BOTOX treatment was not different following seroconversion in these three patients.

In detrusor overactivity associated with neurologic condition patients with analyzable specimens in the adult drug development program (including the open-label extension study), neutralizing antibodies developed in 3 of 300 patients (1.0%) after receiving only BOTOX 200 Unit doses and 5 of 258 patients (1.9%) after receiving at least one 300 Unit dose. Following development of neutralizing antibodies in these 8 patients, 4 continued to experience clinical benefit, 2 did not experience clinical benefit, and the effect on the response to BOTOX in the remaining 2 patients is not known. In 99 pediatric patients who had a negative baseline result for binding antibodies or neutralizing antibodies and had at least one evaluable post-baseline value from one randomized double-blind study and one double-blind extension study, no patients developed neutralizing antibodies after receiving 50 Units to 200 Units of BOTOX.

The data reflect the patients whose test results were considered positive for neutralizing activity to BOTOX in a mouse protection assay or negative based on a screening ELISA assay or mouse protection assay.

Formation of neutralizing antibodies to botulinum toxin type A may reduce the effectiveness of BOTOX treatment by inactivating the biological activity of the toxin. The critical factors for neutralizing antibody formation have not been well characterized. The results from some studies suggest that BOTOX injections at more frequent intervals or at higher doses may lead to greater incidence of antibody formation. The potential for antibody formation may be minimized by injecting with the lowest effective dose given at the longest feasible intervals between injections.

6.3 Postmarketing Experience

The following adverse reactions have been identified during post-approval use of BOTOX. Because these reactions are reported voluntarily from a population of uncertain size, it is not always possible to reliably estimate their frequency or establish a causal relationship to drug exposure. These reactions include: abdominal pain; alopecia, including madarosis; anorexia; brachial plexopathy; denervation/muscle atrophy; diarrhea; dry eye; eyelid edema (following periocular injection); hyperhidrosis; hypoacusis; hypoaesthesia; localized muscle twitching; malaise; Mephisto sign; paresthesia; peripheral neuropathy; radiculopathy; erythema multiforme, dermatitis psoriasiform, and psoriasiform eruption; strabismus; tinnitus; and visual disturbances.

There have been spontaneous reports of death, sometimes associated with dysphagia, pneumonia, and/or other significant debility or anaphylaxis, after treatment with botulinum toxin [see Warnings and Precautions (5.4,5.6)].

There have also been reports of adverse events involving the cardiovascular system, including arrhythmia and myocardial infarction, some with fatal outcomes. Some of these patients had risk factors including cardiovascular disease. The exact relationship of these events to the botulinum toxin injection has not been established.

New onset or recurrent seizures have also been reported, typically in patients who are predisposed to experiencing these events. The exact relationship of these events to the botulinum toxin injection has not been established.

7 DRUG INTERACTIONS

7.1 Aminoglycosides and Other Agents Interfering with Neuromuscular Transmission

Co-administration of BOTOX and aminoglycosides or other agents interfering with neuromuscular transmission (e.g., curare-like compounds) should only be performed with caution as the effect of the toxin may be potentiated.

7.2 Anticholinergic Drugs

Use of anticholinergic drugs after administration of BOTOX may potentiate systemic anticholinergic effects.

7.3 Other Botulinum Neurotoxin Products

The effect of administering different botulinum neurotoxin products at the same time or within several months of each other is unknown. Excessive neuromuscular weakness may be exacerbated by administration of another botulinum toxin prior to the resolution of the effects of a previously administered botulinum toxin.

7.4 Muscle Relaxants

Excessive weakness may also be exaggerated by administration of a muscle relaxant before or after administration of BOTOX.

8 USE IN SPECIFIC POPULATIONS

8.1 Pregnancy

Risk Summary

There are no studies or adequate data from postmarketing surveillance on the developmental risk associated with use of BOTOX in pregnant women. In animal studies, administration of BOTOX during pregnancy resulted in adverse effects on fetal growth (decreased fetal weight and skeletal ossification) at clinically relevant doses, which were associated with maternal toxicity [see Data].

In the U.S. general population, the estimated background risk of major birth defects and miscarriages in clinically recognized pregnancies is 2-4% and 15-20%, respectively. The background risk of major birth defects and miscarriage for the indicated populations is unknown.

Data

Animal Data

When BOTOX (4, 8, or 16 Units/kg) was administered intramuscularly to pregnant mice or rats two times during the period of organogenesis (on gestation days 5 and 13), reductions in fetal body weight and decreased fetal skeletal ossification were observed at the two highest doses. The no-effect dose for developmental toxicity in these studies (4 Units/kg) is approximately equal to the human dose of 400 Units, on a body weight basis (Units/kg).

When BOTOX was administered intramuscularly to pregnant rats (0.125, 0.25, 0.5, 1, 4, or 8 Units/kg) or rabbits (0.063, 0.125, 0.25, or 0.5 Units/kg) daily during the period of organogenesis (total of 12 doses in rats, 13 doses in rabbits), reduced fetal body weights and decreased fetal skeletal ossification were observed at the two highest doses in rats and at the highest dose in rabbits. These doses were also associated with significant maternal toxicity, including abortions, early deliveries, and maternal death. The developmental no-effect doses in these studies of 1 Unit/kg in rats and 0.25 Units/kg in rabbits are less than the human dose of 400 Units, based on Units/kg.

When pregnant rats received single intramuscular injections (1, 4, or 16 Units/kg) at three different periods of development (prior to implantation, implantation, or organogenesis), no adverse effects on fetal development were observed. The developmental no-effect level for a single maternal dose in rats (16 Units/kg) is approximately 2 times the human dose of 400 Units, based on Units/kg.

8.2 Lactation

Risk Summary

There are no data on the presence of BOTOX in human or animal milk, the effects on the breastfed infant, or the effects on milk production. The developmental and health benefits of breastfeeding should be considered along with the mother’s clinical need for BOTOX and any potential adverse effects on the breastfed infant from BOTOX or from the underlying maternal conditions.

8.4 Pediatric Use

Detrusor Overactivity associated with a Neurologic Condition

The safety and effectiveness of BOTOX for detrusor overactivity associated with a neurologic condition have been established in pediatric patients 5 years of age and older who have an inadequate response to or are intolerant of anticholinergic medication. Use of BOTOX in this patient population is based on the results of a randomized, double-blind, parallel group trial in 113 pediatric patients 5 to 17 years of age (inclusive) with detrusor overactivity associated with a neurologic condition (Study 191622-120) and a long-term, multicenter, double-blind, long-term extension trial (Study 191622-121) [see Clinical Studies (14.3)].The most common adverse reactions in this population were urinary tract infection, bacteriuria, hematuria, and leukocyturia [see Adverse Reactions (6.1)].

The safety and effectiveness of BOTOX have not been established in patients with NDO younger than 5 years of age.

Overactive Bladder

The safety and effectiveness of BOTOX for the treatment of overactive bladder have not been established in pediatric patients.

Efficacy was not demonstrated in a multicenter, randomized, double-blind, parallel-group, multiple-dose clinical study which was conducted to evaluate the efficacy and safety of BOTOX in pediatric patients aged 12 to 17 years with overactive bladder. Fifty-five patients who had an inadequate response to or were intolerant of at least one anticholinergic medication were treated with BOTOX. There was not a statistically significant difference in the mean change from baseline in the daily average frequency of daytime urinary incontinence episodes (primary efficacy endpoint) at week 12 post-treatment when a medium and high dose were each compared to a low dose of BOTOX. The adverse reactions in pediatric patients treated with BOTOX were comparable with the known safety profile in adults with overactive bladder.

Prophylaxis of Headaches in Chronic Migraine

Safety and effectiveness in patients below the age of 18 years have not been established.

In a 12-week, multicenter, double-blind, placebo-controlled clinical trial, 123 adolescent patients (ages 12 to below 18 years) with chronic migraine were randomized to receive BOTOX 74 Units, BOTOX 155 Units, or placebo, for one injection cycle. This trial did not establish the efficacy of BOTOX, compared with placebo, for the prophylaxis of headaches in adolescents with chronic migraine.

Spasticity

Safety and effectiveness have been established in pediatric patients 2 to 17 years of age [see Warnings and Precautions (5.1), Adverse Reactions (6.1), and Clinical Studies (14.6)]. The safety and effectiveness of BOTOX have been established by evidence from adequate and well-controlled studies of BOTOX in patients 2 to 17 years of age with upper and lower limb spasticity.

Safety and effectiveness in pediatric patients below the age of 2 years have not been established [see Boxed Warningand Warnings and Precautions (5.1)].

Axillary Hyperhidrosis

Safety and effectiveness in patients below the age of 18 years have not been established.

Cervical Dystonia

Safety and effectiveness in pediatric patients below the age of 16 years have not been established.

Blepharospasm and Strabismus

Safety and effectiveness in pediatric patients below the age of 12 years have not been established.

Juvenile Animal Data

In a study in which juvenile rats received intramuscular injection of BOTOX (0, 8, 16, or 24 Units/kg) every other week from postnatal day 21 for 12 weeks, changes in bone size/geometry associated with decreased bone density and bone mass were observed at all doses, in association with limb disuse, decreased muscle contraction, and decreased body weight gain. Impairment of fertility and male reproductive organ histopathology (degeneration of seminiferous tubules of the testis) were observed at the mid and high doses. Bone and male reproductive organ effects showed evidence of reversibility after dosing cessation. The no-effect dose for adverse developmental effects in juvenile animals (8 Units/kg) is similar to the human dose (400 Units) on a body weight (kg) basis.

8.5 Geriatric Use

Of the 2145 adult patients in placebo-controlled clinical studies of BOTOX for the treatment of spasticity, 33.5% were 65 or older, and 7.7% were 75 years of age or older. No overall differences in safety were observed between elderly patients and adult patients younger than 65 years of age.

In clinical studies of BOTOX across other indications, no overall differences in safety were observed between elderly patients and younger adult patients, with the exception of Overactive Bladder (see below). Other reported clinical experience has not identified differences in responses between the elderly and younger adult patients, but greater sensitivity of some older individuals cannot be ruled out.

Overactive Bladder

Of 1242 overactive bladder patients in placebo-controlled clinical studies of BOTOX, 41.4% were 65 years of age or older, and 14.7% were 75 years of age or older. Adverse reactions of UTI and urinary retention were more common in patients 65 years of age or older in both placebo and BOTOX groups compared to younger patients (see Table 24). Otherwise, there were no overall differences in the safety profile following BOTOX treatment between patients aged 65 years and older compared to adult patients younger than 65 years of age in these studies.

Table 24: Incidence of Urinary Tract Infection and Urinary Retention according to Age Group during First Placebo-Controlled Treatment, Placebo-Controlled Clinical Trials in Patients with OAB
 | <65 Years |  | 65 to 74 Years |  | ≥75 Years
Adverse Reactions | BOTOX 100 Units (N=344) % | Placebo (N=348) % | BOTOX 100 Units (N=169) % | Placebo (N=151) % | BOTOX 100 Units (N=94) % | Placebo (N=86) %
Urinary tract infection | 21 | 7 | 30 | 13 | 38 | 19
Urinary retention | 6 | 0.6 | 8 | 0 | 9 | 1

Observed effectiveness was comparable between these age groups in placebo-controlled clinical studies.

10 OVERDOSAGE

Excessive doses of BOTOX (onabotulinumtoxinA) for injection may be expected to produce neuromuscular weakness with a variety of symptoms.

Symptoms of overdose are likely not to be present immediately following injection. Should accidental injection or oral ingestion occur or overdose be suspected, the person should be medically supervised for several weeks for signs and symptoms of systemic muscular weakness which could be local, or distant from the site of injection [see Boxed Warningand Warnings and Precautions (5.1,5.6)]. These patients should be considered for further medical evaluation and appropriate medical therapy immediately instituted, which may include hospitalization.

If the musculature of the oropharynx and esophagus are affected, aspiration may occur which may lead to development of aspiration pneumonia. If the respiratory muscles become paralyzed or sufficiently weakened, intubation and assisted respiration may be necessary until recovery takes place. Supportive care could involve the need for a tracheostomy and/or prolonged mechanical ventilation, in addition to other general supportive care.

In the event of overdose, antitoxin raised against botulinum toxin is available from the Centers for Disease Control and Prevention (CDC) in Atlanta, GA. However, the antitoxin will not reverse any botulinum toxin-induced effects already apparent by the time of antitoxin administration. In the event of suspected or actual cases of botulinum toxin poisoning, please contact your local or state Health Department to process a request for antitoxin through the CDC. If you do not receive a response within 30 minutes, please contact the CDC directly at 1-770-488-7100. More information can be obtained at http://www.cdc.gov/mmwr/preview/mmwrhtml/mm5232a8.htm.

11 DESCRIPTION

OnabotulinumtoxinA is a sterile, vacuum-dried purified botulinum toxin type A, produced from fermentation of Hall strain Clostridium botulinumtype A, and intended for intramuscular, intradetrusor and intradermal use. It is purified from the culture solution by dialysis and a series of acid precipitations to a complex consisting of the neurotoxin, and several accessory proteins. The complex is dissolved in sterile sodium chloride solution containing Albumin Human and is sterile filtered (0.2 microns) prior to filling and vacuum-drying.

The primary release procedure for BOTOX uses a cell-based potency assay to determine the potency relative to a reference standard. The assay is specific to AbbVie’s products BOTOX and BOTOX Cosmetic. One Unit of BOTOX corresponds to the calculated median intraperitoneal lethal dose (LD50) in mice. Due to specific details of this assay such as the vehicle, dilution scheme, and laboratory protocols, Units of biological activity of BOTOX cannot be compared to nor converted into Units of any other botulinum toxin or any toxin assessed with any other specific assay method. The specific activity of BOTOX is approximately 20 Units/nanogram of neurotoxin protein complex.

Each vial of BOTOX (onabotulinumtoxinA) for injection contains either 100 Units of Clostridium botulinum type A neurotoxin complex, 0.5 mg of Albumin Human, and 0.9 mg of sodium chloride in a sterile, vacuum-dried form without a preservative.

12 CLINICAL PHARMACOLOGY

12.1 Mechanism of Action

BOTOX blocks neuromuscular transmission by binding to acceptor sites on motor or autonomic nerve terminals, entering the nerve terminals, and inhibiting the release of acetylcholine. This inhibition occurs as the neurotoxin cleaves SNAP-25, a protein integral to the successful docking and release of acetylcholine from vesicles situated within nerve endings. When injected intramuscularly at therapeutic doses, BOTOX produces partial chemical denervation of the muscle resulting in a localized reduction in muscle activity. In addition, the muscle may atrophy, axonal sprouting may occur, and extrajunctional acetylcholine receptors may develop. There is evidence that reinnervation of the muscle may occur, thus slowly reversing muscle denervation produced by BOTOX.

When injected intradermally, BOTOX produces temporary chemical denervation of the sweat gland resulting in local reduction in sweating.

Following intradetrusor injection, BOTOX affects the efferent pathways of detrusor activity via inhibition of acetylcholine release.

12.3 Pharmacokinetics

Using currently available analytical technology, it is not possible to detect BOTOX in the peripheral blood following intramuscular injection at the recommended doses.

13 NONCLINICAL TOXICOLOGY

13.1 Carcinogenesis, Mutagenesis, Impairment of Fertility

Carcinogenesis

Long term studies in animals have not been performed to evaluate the carcinogenic potential of BOTOX.

Mutagenesis

BOTOX was negative in a battery of in vitro (microbial reverse mutation assay, mammalian cell mutation assay, and chromosomal aberration assay) and in vivo (micronucleus assay) genetic toxicology assays.

Impairment of Fertility

In fertility studies of BOTOX (4, 8, or 16 Units/kg) in which either male or female rats were injected intramuscularly prior to mating and on the day of mating (3 doses, 2 weeks apart for males: 2 doses, 2 weeks apart for females) to untreated animals, reduced fertility was observed in males at the intermediate and high doses and in females at the high dose. The no-effect doses for reproductive toxicity (4 Units/kg in males, 8 Units/kg in females) are approximately equal to the human dose of 400 Units, on a body weight basis (Units/kg).

13.2 Animal Toxicologyand/or Pharmacology

In a study to evaluate inadvertent peribladder administration, bladder stones were observed in 1 of 4 male monkeys that were injected with a total of 6.8 Units/kg divided into the prostatic urethra and proximal rectum (single administration). No bladder stones were observed in male or female monkeys following injection of up to 36 Units/kg (~12X the highest human bladder dose) directly to the bladder as either single or 4 repeat dose injections or in female rats for single injections up to 100 Units/kg (~33X the highest human bladder dose [200 Units], based on Units/kg).

14 CLINICAL STUDIES

14.1 Overactive Bladder (OAB)

Two double-blind, placebo-controlled, randomized, multi-center, 24-week clinical studies were conducted in patients with OAB with symptoms of urge urinary incontinence, urgency, and frequency (Studies OAB-1 and OAB-2). Patients needed to have at least 3 urinary urgency incontinence episodes and at least 24 micturitions in 3 days to enter the studies. A total of 1105 patients, whose symptoms had not been adequately managed with anticholinergic therapy (inadequate response or intolerable side effects), were randomized to receive either 100 Units of BOTOX (n=557), or placebo (n=548). Patients received 20 injections of study drug (5 Units of BOTOX or placebo) spaced approximately 1 cm apart into the detrusor muscle.

In both studies, significant improvements compared to placebo in the primary efficacy variable of change from baseline in daily frequency of urinary incontinence episodes were observed for BOTOX 100 Units at the primary time point of week 12. Significant improvements compared to placebo were also observed for the secondary efficacy variables of daily frequency of micturition episodes and volume voided per micturition. These primary and secondary variables are shown in Table 25 and Table 26, and Figure 7 and Figure 8.

Table 25: Baseline and Change from Baseline in Urinary Incontinence Episode Frequency, Micturition Episode Frequency and Volume Voided Per Micturition, Study OAB-1
 | BOTOX 100 Units (N=278) | Placebo (N=272) | Treatment Difference | p-value
Daily Frequency of Urinary Incontinence Episodesa
Mean Baseline | 5.5 | 5.1
Mean Change*at Week 2 | -2.6 | -1.0 | -1.6
Mean Change*at Week 6 | -2.8 | -1.0 | -1.8
Mean Change*at Week 12** | -2.5 | -0.9 | -1.6 (-2.1, -1.2) | <0.001
Daily Frequency of Micturition Episodesb
Mean Baseline | 12.0 | 11.2
Mean Change†at Week 12** | -1.9 | -0.9 | -1.0 (-1.5, -0.6) | <0.001
Volume Voided per Micturitionb (mL)
Mean Baseline | 156 | 161
Mean Change†at Week 12** | 38 | 8 | 30 (17, 43) | <0.001

*Least squares (LS) mean change, treatment difference and p-value are based on an ANCOVA model with baseline value as covariate and treatment group and investigator as factors. Last observation carried forward (LOCF) values were used to analyze the primary efficacy variable.

†LS mean change, treatment difference and p-value are based on an ANCOVA model with baseline value as covariate and stratification factor, treatment group and investigator as factors.

**Primary timepoint

aPrimary variable

bSecondary variable

Table 26: Baseline and Change from Baseline in Urinary Incontinence Episode Frequency, Micturition Episode Frequency and Volume Voided Per Micturition, Study OAB-2
 | BOTOX 100 Units (N=275) | Placebo (N=269) | Treatment Difference | p-value
Daily Frequency of Urinary Incontinence Episodesa
Mean Baseline | 5.5 | 5.7
Mean Change*at Week 2 | -2.7 | -1.1 | -1.6
Mean Change*at Week 6 | -3.1 | -1.3 | -1.8
Mean Change*at Week 12** | -3.0 | -1.1 | -1.9 (-2.5, -1.4) | <0.001
Daily Frequency of Micturition Episodesb
Mean Baseline | 12.0 | 11.8
Mean Change†at Week 12** | -2.3 | -0.6 | -1.7 (-2.2, -1.3) | <0.001
Volume Voided per Micturitionb (mL)
Mean Baseline | 144 | 153
Mean Change†at Week 12** | 40 | 10 | 31 (20, 41) | <0.001

*LS mean change, treatment difference and p-value are based on an ANCOVA model with baseline value as covariate and treatment group and investigator as factors. LOCF values were used to analyze the primary efficacy variable.

† LS mean change, treatment difference and p-value are based on an ANCOVA model with baseline value as covariate and stratification factor, treatment group and investigator as factors.

**Primary timepoint

aPrimary variable

bSecondary variable

Figure 7: Mean Change from Baseline in Daily Frequency of Urinary Incontinence Episodes Following Intradetrusor Injection in Study OAB-1

Figure 8: Mean Change from Baseline in Daily Frequency of Urinary Incontinence Episodes Following Intradetrusor Injection in Study OAB-2

The median duration of response in Study OAB-1 and OAB-2, based on patient qualification for re-treatment, was 19-24 weeks for the BOTOX 100 Unit dose group compared to 13 weeks for placebo. To qualify for re-treatment, at least 12 weeks must have passed since the prior treatment, post-void residual urine volume must have been less than 200 mL and patients must have reported at least 2 urinary incontinence episodes over 3 days.

14.2 Adult Detrusor Overactivity Associatedwith a Neurologic Condition

Two double-blind, placebo-controlled, randomized, multi-center clinical studies were conducted in patients with urinary incontinence due to detrusor overactivity associated with a neurologic condition who were either spontaneously voiding or using catheterization (Studies NDO-1 and NDO-2). A total of 691 spinal cord injury (T1 or below) or multiple sclerosis patients, who had an inadequate response to or were intolerant of at least one anticholinergic medication, were enrolled. These patients were randomized to receive either 200 Units of BOTOX (n=227), 300 Units of BOTOX (n=223), or placebo (n=241).

In both studies, significant improvements compared to placebo in the primary efficacy variable of change from baseline in weekly frequency of incontinence episodes were observed for BOTOX (200 Units) at the primary efficacy time point at week 6. Increases in maximum cystometric capacity and reductions in maximum detrusor pressure during the first involuntary detrusor contraction were also observed. These primary and secondary endpoints are shown in Table 27 and Table 28, and Figure 9 and Figure 10.

No additional benefit of BOTOX 300 Units over 200 Units was demonstrated.

Table 27: Baseline and Change from Baseline in Weekly Urinary Incontinence Episode Frequency, Maximum Cystometric Capacity and Maximum Detrusor Pressure during First Involuntary Detrusor Contraction (cmH2O) Study NDO-1
 | BOTOX 200 Units | Placebo | Treatment Difference* | p-value*
Weekly Frequency of Urinary Incontinence Episodesa
N | 134 | 146
Mean Baseline | 32.3 | 28.3
Mean Change* at Week 2 | -15.3 | -10.0 | -5.3 | ─
Mean Change* at Week 6** | -19.9 | -10.6 | -9.2 | p<0.001
 |  |  | (-13.1, -5.3)
Mean Change* at Week 12 | -19.8 | -8.8 | -11.0 | ─
Maximum Cystometric Capacityb (mL)
N | 123 | 129
Mean Baseline | 253.8 | 259.1
Mean Change* at Week 6** | 135.9 | 12.1 | 123.9 | p<0.001
 |  |  | (89.1, 158.7)
Maximum Detrusor Pressure during First Involuntary Detrusor Contraction b (cmH 2 O)
N | 41 | 103
Mean Baseline | 63.1 | 57.4
Mean Change* at Week 6** | -28.1 | -3.7 | -24.4 | ─

* LS mean change, treatment difference and p-value are based on an analysis using an ANCOVA model with baseline weekly endpoint as covariate and treatment group, etiology at study entry (spinal cord injury or multiple sclerosis), concurrent anticholinergic therapy at screening, and investigator as factors. LOCF values were used to analyze the primary efficacy variable.

** Primary timepoint

aPrimary endpoint

bSecondary endpoint

Table 28: Baseline and Change from Baseline in Weekly Urinary Incontinence Episode Frequency, Maximum Cystometric Capacity and Maximum Detrusor Pressure during First Involuntary Detrusor Contraction (cmH2O) in Study NDO-2
 | BOTOX 200 Units | Placebo | Treatment Difference* | p-value*
Weekly Frequency of Urinary Incontinence Episodesa
N | 91 | 91
Mean Baseline | 32.7 | 36.8
Mean Change* at Week 2 | -18.0 | -7.9 | -10.1 | ─
Mean Change* at Week 6** | -19.6 | -10.8 | -8.8 | p=0.003
 |  |  | (-14.5, -3.0)
Mean Change* at Week 12 | -19.6 | -10.7 | -8.9 | ─
Maximum Cystometric Capacityb (mL)
N | 88 | 85
Mean Baseline | 239.6 | 253.8
Mean Change* at Week 6** | 150.8 | 2.8 | 148.0 | p<0.001
 |  |  | (101.8, 194.2)
Maximum Detrusor Pressure during First Involuntary Detrusor Contractionb (cmH 2 O)
N | 29 | 68
Mean Baseline | 65.6 | 43.7
Mean Change* at Week 6** | -28.7 | 2.1 | -30.7 | ─

* LS mean change, treatment difference and p-value are based on an analysis using an ANCOVA model with baseline weekly endpoint as covariate and treatment group, etiology at study entry (spinal cord injury or multiple sclerosis), concurrent anticholinergic therapy at screening, and investigator as factors. LOCF values were used to analyze the primary efficacy variable.

** Primary timepoint

aPrimary endpoint

bSecondary endpoint

Figure 9: Mean Change from Baseline in Weekly Frequency of Urinary Incontinence Episodes During Treatment Cycle 1 in Study NDO-1

Figure 10: Mean Change from Baseline in Weekly Frequency of Urinary Incontinence Episodes During Treatment Cycle 1 in Study NDO-2

The median duration of response in study NDO-1 and NDO-2, based on patient qualification for re-treatment was 295-337 days (42-48 weeks) for the 200 Units dose group compared to 96-127 days (13-18 weeks) for placebo. Re-treatment was based on loss of effect on incontinence episode frequency (50% of effect in Study NDO-1; 70% of effect in Study NDO-2).

A placebo-controlled, double-blind randomized post-approval 52 week study (Study NDO-3) was conducted in MS patients with urinary incontinence due to neurogenic detrusor overactivity who were not adequately managed with at least one anticholinergic agent and not catheterizing at baseline. These patients were randomized to receive either 100 Units of BOTOX (n=66) or placebo (n=78).

Significant improvements compared to placebo in the primary efficacy variable of change from baseline in daily frequency of incontinence episodes were observed for BOTOX (100 Units) at the primary efficacy time point at week 6. Increases in maximum cystometric capacity and reductions in maximum detrusor pressure during the first involuntary detrusor contraction were also observed. These primary and secondary endpoints are shown in Table 29.

Table 29: Baseline and Change from Baseline in Daily Urinary Incontinence Episode Frequency, Maximum Cystometric Capacity and Maximum Detrusor Pressure during First Involuntary Detrusor Contraction (cmH2O) in Study NDO-3
 | BOTOX 100 Units | Placebo | Treatment Difference* | p-value*
Daily Frequency of Urinary Incontinence Episodesa
N | 66 | 78
Mean Baseline | 4.2 | 4.3
Mean Change* at Week 2 | -2.9 | -1.2 | -1.7 | ─
Mean Change* at Week 6** | -3.4 | -1.1 | -2.3 | p<0.001
 |  |  | (-3.0, -1.7)
Mean Change* at Week 12 | -2.7 | -1.0 | -1.8 | ─
Maximum Cystometric Capacityb (mL)
N | 62 | 72
Mean Baseline | 248.9 | 245.5
Mean Change* at Week 6** | 134.4 | 3.5 | 130.9 | p<0.001
 |  |  | (94.8, 167.0)
Maximum Detrusor Pressure during First Involuntary Detrusor Contractionb (cmH 2 O)
N | 25 | 51
Mean Baseline | 42.4 | 39.0
Mean Change* at Week 6** | -19.2 | 2.7 | -21.9
 |  |  | (-37.5, -6.3)

* LS mean change, treatment difference and p-value are based on an analysis using an ANCOVA model with baseline daily endpoint as covariate and treatment group and propensity score stratification as factors. LOCF values were used to analyze the primary efficacy variable.

** Primary timepoint

aPrimary endpoint

bSecondary endpoint

The median duration of response in study NDO-3, based on patient qualification for re-treatment was 362 days (52 weeks) for the BOTOX 100 Units dose group compared to 88 days (13 weeks) for placebo. To qualify for re-treatment, at least 12 weeks must have passed since the prior treatment, post-void residual urine volume must have been less than 200 mL and patients must have reported at least 2 urinary incontinence episodes over 3 days with no more than 1 incontinence-free day.

14.3 Pediatric Detrusor Overactivity Associated with a Neurologic Condition

Study 191622-120 (NCT01852045) was a multicenter, randomized, double-blind, parallel-group clinical study conducted in patients 5 to 17 years of age with urinary incontinence due to detrusor overactivity associated with a neurologic condition and using clean intermittent catheterization. A total of 113 patients (including 99 with spinal dysraphism such as spina bifida, 13 with spinal cord injury and 1 with transverse myelitis) who had an inadequate response to or were intolerant of at least one anticholinergic medication were enrolled. The median age was 11 years (range: 5 to 17 years), 49% were female; 75% were White, 10% were Black. These patients were randomized to 50 Units, 100 Units or 200 Units, not to exceed 6 Units/kg body weight. Patients receiving less than the randomized dose due to the 6 Units/kg maximum, were assigned to the nearest dose group for analysis. The sample size for BOTOX 50 Units, 100 Units, and 200 Units were 38, 45 and 30, respectively. Prior to treatment administration, patients received anesthesia based on age and local site practice. One hundred and nine patients (97.3%) received general anesthesia or conscious sedation and 3 patients (2.7%) received local anesthesia.

The study results demonstrated within group improvements in the primary efficacy variable of change from baseline in daytime urinary incontinence episodes (normalized to 12 hours) at the primary efficacy time point (Week 6) for all 3 BOTOX treatment groups. Additional benefits were seen with BOTOX 200 Units for measures related to reducing maximum bladder pressure when compared to 50 Units. The decrease in maximum detrusor pressure (MDP) during the storage phase (MDP defined as the highest value in the Pdet channel during the storage phase [e.g., the greater of the following: the maximum Pdet during the highest amplitude IDC, the maximum Pdet during a terminal detrusor contraction, the Pdet at the end of filling, or the highest Pdet at any other time during the storage phase]) for BOTOX 200 Units at Week 6 was greater than the decrease observed for 50 Units. Within group improvements for the primary and secondary endpoints for the 200 Units dose group are shown in Table 30.

The efficacy of BOTOX 6 U/kg for pediatric patients with NDO weighing less than 34 kg was comparable to that of BOTOX 200 U.

Table 30: Baseline and Change from Baseline in Daily Daytime Frequency of Urinary Incontinence Episodes, Urine Volume at First Morning Catheterization, Maximum Detrusor Pressure during the Storage Phase (cmH2O), and Maximum Cystometric Capacity (mL) in Study191622-120
 | BOTOX 200 U N=30
Daily average frequency of daytime urinary incontinence episodesa
Mean Baseline | 3.7
Mean Change* at Week 2 (95% CI) | -1.1 (-1.7, -0.6)
Mean Change* at Week 6** (95% CI) | -1.3 (-1.8, -0.9)
Mean Change* at Week 12 (95% CI) | -0.9 (-1.5, -0.4)
Urine Volume at First Morning Catheterization (mL)ᵇ
Mean Baseline | 187.7
Mean Change* at Week 2 (95% CI) | 63.2 (27.9, 98.6)
Mean Change* at Week 6** (95% CI) | 87.5 (52.1, 122.8)
Mean Change* at Week 12 (95% CI) | 45.2 (10.0, 80.5)
Maximum Detrusor Pressure (PdetMax) During the Storage Phase (cm H2O)ᵇ
Mean Baseline | 56.7
Mean Change* at Week 6** (95% CI) | -27.3 (-36.4, -18.2)
Maximum Cystometric Capacity (mL) (MCC)ᵇ
Mean Baseline | 202.3
Mean Change* at Week 6** (95% CI) | 63.6 (29.0, 98.1)

CI = Confidence Interval

* LSmean change and 95% CI are based on an ANCOVA model with baseline value as covariate and treatment group, age (< 12 years or >= 12 years), baseline daytime urinary incontinence episodes (<= 6 or > 6) and anticholinergic therapy (yes/no) at baseline as factors.

** Primary timepoint

aPrimary endpoint

bSecondary endpoint

The median duration of response in this study, based on patient qualification for re-treatment was 207 days (30 weeks) for BOTOX 200 Units dose group. To qualify for re-treatment, patients must have reported at least 2 urinary incontinence episodes over 2 days and at least 12 weeks have passed from the prior bladder injection.

14.4 Chronic Migraine

BOTOX was evaluated in two randomized, multi-center, 24-week, 2 injection cycle, placebo-controlled double-blind studies. Study 1 and Study 2 included chronic migraine adults who were not using any concurrent headache prophylaxis, and during a 28-day baseline period had >15 headache days lasting 4 hours or more, with >50% being migraine/probable migraine. In both studies, patients were randomized to receive placebo or 155 Units to 195 Units BOTOX injections every 12 weeks for the 2-cycle, double-blind phase. Patients were allowed to use acute headache treatments during the study. BOTOX treatment demonstrated statistically significant and clinically meaningful improvements from baseline compared to placebo for key efficacy variables (see Table 31).

Table 31: Week 24 Key Efficacy Variables for Study 1 and Study 2
Efficacy per 28 days | Study 1 |  | Study 2
 | BOTOX (N=341) | Placebo (N=338) | BOTOX (N=347) | Placebo (N=358)
Change from baseline in frequency of headache days | -7.8* | -6.4 | -9.2* | -6.9
Change from baseline in total cumulative hours of headache on headache days | -107* | -70 | -134* | -95

*Significantly different from placebo (p <0.05)

Patients treated with BOTOX had a significantly greater mean decrease from baseline in the frequency of headache days at most timepoints from Week 4 to Week 24 in Study 1 (Figure 11), and all timepoints from Week 4 to Week 24 in Study 2 (Figure 12), compared to placebo-treated patients.

Figure 11: Mean Change from Baseline in Number of Headache Days for Study 1

Figure 12: Mean Change from Baseline in Number of Headache Days for Study 2

14.5 Adult Spasticity

Adult Upper Limb Spasticity

The efficacy of BOTOX for the treatment of adult upper limb spasticity was evaluated in several randomized, multi-center, double-blind, placebo-controlled studies (Studies 1 through 6).

Study 1 included 126 adult patients (64 BOTOX and 62 placebo) with upper limb spasticity (Ashworth score of at least 3 for wrist flexor tone and at least 2 for finger flexor tone) who were at least 6 months post-stroke. BOTOX (a total dose of 200 Units to 240 Units) and placebo were injected intramuscularly (IM) into the flexor digitorum profundus, flexor digitorum sublimis, flexor carpi radialis, flexor carpi ulnaris, and if necessary into the adductor pollicis and flexor pollicis longus (see Table 32). Use of an EMG/nerve stimulator was recommended to assist in proper muscle localization for injection. Patients were followed for 12 weeks.

Table 32: BOTOX Dose and Injection Sites in Study 1
Muscles Injected | Volume (mL) | BOTOX (Units) | Number of Injection Sites
Wrist Flexor Carpi Radialis | 1 | 50 | 1
Flexor Carpi Ulnaris | 1 | 50 | 1
Finger Flexor Digitorum Profundus | 1 | 50 | 1
Flexor Digitorum Sublimis | 1 | 50 | 1
Thumb Adductor Pollicisa | 0.4 | 20 | 1
Flexor Pollicis Longusa | 0.4 | 20 | 1

a Injected only if spasticity is present in this muscle

The primary efficacy variable was wrist flexors muscle tone at week 6, as measured by the Ashworth score. The Ashworth Scale is a 5-point scale with grades of 0 [no increase in muscle tone] to 4 [limb rigid in flexion or extension]. It is a clinical measure of the force required to move an extremity around a joint, with a reduction in score clinically representing a reduction in the force needed to move a joint (i.e., improvement in spasticity).

Key secondary endpoints included Physician Global Assessment, finger flexors muscle tone, and thumb flexors tone at Week 6. The Physician Global Assessment evaluated the response to treatment in terms of how the patient was doing in his/her life using a scale from -4 = very marked worsening to +4 = very marked improvement. Study 1 results on the primary endpoint and the key secondary endpoints are shown in Table 33.

Table 33: Primary and Key Secondary Endpoints by Muscle Group at Week 6 in Study 1
 | BOTOX (N=64) | Placebo (N=62)
Median Change from Baseline in Wrist Flexor Muscle Tone on the Ashworth Scale†a | -2.0* | 0.0
Median Change from Baseline in Finger Flexor Muscle Tone on the Ashworth Scale††b | -1.0* | 0.0
Median Change from Baseline in Thumb Flexor Muscle Tone on the Ashworth Scale††c | -1.0 | -1.0
Median Physician Global Assessment of Response to Treatment†† | 2.0* | 0.0

†Primary endpoint at Week 6

††Secondary endpoints at Week 6

*Significantly different from placebo (p <0.05)

aBOTOX injected into both the flexor carpi radialis and ulnaris muscles

bBOTOXinjected into the flexor digitorum profundus and flexor digitorum sublimis muscles

cBOTOX injected into the adductor pollicis and flexor pollicis longus muscles

Study 2 compared 3 doses of BOTOX with placebo and included 91 adult patients [BOTOX 360 Units (N=21), BOTOX 180 Units (N=23), BOTOX 90 Units (N=21), and placebo (N=26)] with upper limb spasticity (expanded Ashworth score of at least 2 for elbow flexor tone and at least 3 for wrist flexor tone) who were at least 6 weeks post-stroke. BOTOX and placebo were injected with EMG guidance into the flexor digitorum profundus, flexor digitorum sublimis, flexor carpi radialis, flexor carpi ulnaris, and biceps brachii (see Table 34).

Table 34: BOTOX Dose and Injection Sites in Study 2 and Study 3
 | Total Dose
Muscles Injected | BOTOX low dose (90 Units) | BOTOX mid dose (180 Units) | BOTOX high dose (360 Units) | Volume (mL) per site | Injection Sites (n)
Wrist Flexor Carpi Ulnaris | 10 Units | 20 Units | 40 Units | 0.4 | 1
Flexor Carpi Radialis | 15 Units | 30 Units | 60 Units | 0.6 | 1
Finger Flexor Digitorum Profundus | 7.5 Units | 15 Units | 30 Units | 0.3 | 1
Flexor Digitorum Sublimis | 7.5 Units | 15 Units | 30 Units | 0.3 | 1
Elbow Biceps Brachii | 50 Units | 100 Units | 200 Units | 0.5 | 4

The primary efficacy variable in Study 2 was the wrist flexor tone at Week 6 as measured by the expanded Ashworth Scale. The expanded Ashworth Scale uses the same scoring system as the Ashworth Scale, but allows for half-point increments.

Key secondary endpoints in Study 2 included Physician Global Assessment, finger flexors muscle tone, and elbow flexors muscle tone at Week 6. Study 2 results on the primary endpoint and the key secondary endpoints at Week 6 are shown in Table 35.

Table 35: Primary and Key Secondary Endpoints by Muscle Group and BOTOX Dose at Week 6 in Study 2
 | BOTOX low dose (90 Units) (N=21) | BOTOX mid dose (180 Units) (N=23) | BOTOX high dose (360 Units) (N=21) | Placebo (N=26)
Median Change from Baseline in Wrist Flexor Muscle Tone on the Ashworth Scale†b | -1.5* | -1.0* | -1.5* | -1.0
Median Change from Baseline in Finger Flexor Muscle Tone on the Ashworth Scale††c | -0.5 | -0.5 | -1.0 | -0.5
Median Change from Baseline in Elbow Flexor Muscle Tone on the Ashworth Scale††d | -0.5 | -1.0* | -0.5a | -0.5
Median Physician Global Assessment of Response to Treatment | 1.0* | 1.0* | 1.0* | 0.0

†Primary endpoint at Week 6

††Secondary endpoints at Week 6

*Significantly different from placebo (p <0.05)

ap=0.053

bTotal dose of BOTOX injected into both the flexor carpi radialis and ulnaris muscles

cTotal dose of BOTOXinjected into the flexor digitorum profundus and flexor digitorum sublimis muscles

dDose of BOTOXinjected into biceps brachii muscle

Study 3 compared 3 doses of BOTOX with placebo and enrolled 88 adult patients [BOTOX 360 Units (N=23), BOTOX 180 Units (N=23), BOTOX 90 Units (N=23), and placebo (N=19)] with upper limb spasticity (expanded Ashworth score of at least 2 for elbow flexor tone and at least 3 for wrist flexor tone and/or finger flexor tone) who were at least 6 weeks post-stroke. BOTOX and placebo were injected with EMG guidance into the flexor digitorum profundus, flexor digitorum sublimis, flexor carpi radialis, flexor carpi ulnaris, and biceps brachii (see Table 34).

The primary efficacy variable in Study 3 was wrist and elbow flexor tone as measured by the expanded Ashworth score. A key secondary endpoint was assessment of finger flexors muscle tone. Study 3 results on the primary endpoint at Week 4 are shown in Table 36.

Table 36: Primary and Key Secondary Endpoints by Muscle Group and BOTOX Dose at Week 4 in Study 3
 | BOTOXlow dose (90 Units) (N=23) | BOTOXmid dose (180 Units) (N=21) | BOTOXhigh dose (360 Units) (N=22) | Placebo (N=19)
Median Change from Baseline in Wrist Flexor Muscle Tone on the Ashworth Scale†b | -1.0 | -1.0 | -1.5* | -0.5
Median Change from Baseline in Finger Flexor Muscle Tone on the Ashworth Scale††c | -1.0 | -1.0 | -1.0* | -0.5
Median Change from Baseline in Elbow Flexor Muscle Tone on the Ashworth Scale†d | -0.5 | -0.5 | -1.0* | -0.5

†Primary endpoint at Week 4

††Secondary endpoints at Week 4

*Significantly different from placebo (p <0.05)

bTotal dose of BOTOXinjected into both the flexor carpi radialis and ulnaris muscles

cTotal dose of BOTOXinjected into the flexor digitorum profundus and flexor digitorum sublimis muscles

dDose of BOTOXinjected into biceps brachii muscle

Study 4 (NCT01153815) included 170 adult patients (87 BOTOX and 83 placebo) with upper limb spasticity who were at least 6 months post-stroke. In Study 4, patients received 20 Units of BOTOX into the adductor pollicis and flexor pollicis longus (total BOTOX dose = 40 Units in thumb muscles) or placebo (see Table 37). Study 5 (NCT00460564) included 109 patients with upper limb spasticity who were at least 6 months post-stroke. In Study 5, adult patients received 15 Units (low dose) or 20 Units (high dose) of BOTOX into the adductor pollicis and flexor pollicis longus under EMG guidance (total BOTOX low dose = 30 Units, total BOTOX high dose = 40 Units), or placebo (see Table 37). The duration of follow-up in Study 4 and Study 5 was 12 weeks.

Table 37: BOTOX Dose and Injection Sites in Studies 4 and 5
 | Study 4 |  | Study 5
Muscles Injected | BOTOX (Units) | Volume (mL) | BOTOX low dose (Units) | BOTOX high dose (Units) | Volume low dose (mL) | Volume high dose (mL) | Number of Injection Sites for Studies 4 and 5
Thumb Adductor Pollicis | 20 | 0.4 | 15 | 20 | 0.3 | 0.4 | 1
Flexor Pollicis Longus | 20 | 0.4 | 15 | 20 | 0.3 | 0.4 | 1

The results of Study 4 for the change from Baseline to Week 6 in thumb flexor tone measured by modified Ashworth Scale (MAS) and overall treatment response by Physician Global Assessment at week 6 are presented in Table 38. The MAS uses a similar scoring system as the Ashworth Scale.

Table 38: Efficacy Endpoints for Thumb Flexors at Week 6 in Study 4
 | BOTOX (N=66) | Placebo (N=57)
Median Change from Baseline in Thumb Flexor Muscle Tone on the modified Ashworth Scale††a | -1.0* | 0.0
Median Physician Global Assessment of Response to Treatment†† | 2.0* | 0.0

††Secondary endpoints at Week 6

*Significantly different from placebo (p <0.001)

aBOTOX injected into the adductor pollicis and flexor pollicis longus muscles

In Study 5, the results of the change from Baseline to Week 6 in thumb flexor tone measured by modified Ashworth Scale and Clinical Global Impression (CGI) of functional assessment scale assessed by the physician using an 11-point Numeric Rating Scale [-5 worst possible function to +5 best possible function] are presented in Table 39.

Table 39: Efficacy Endpoints for Thumb Flexors at Week 6 in Study 5
 | BOTOX low dose (30 Units) (N=14) | Placebo low dose (N=9) | BOTOX high dose (40 Units) (N=43) | Placebo high dose (N=23)
Median Change from Baseline in Thumb Flexor Muscle Tone on the modified Ashworth Scale†††a | -1.0 | -1.0 | -0.5* | 0.0
Median Changefrom Baseline in Clinical Global Impression Score by Physician†† | 1.0 | 0.0 | 2.0* | 0.0

††Secondary endpoint at Week 6

†††Other endpoint at Week 6

*Significantly different from placebo (p <0.010)

aBOTOX injected into the adductor pollicis and flexor pollicis longus muscles

Study 6 (NCT03261167) enrolled 124 post-stroke adult patients with upper limb spasticity. In Study 6, 61 patients received 160 Units BOTOX divided among 3 elbow flexors (biceps brachii, brachioradialis, and brachialis) and 63 patients received placebo (see Table 40). EMG, nerve stimulation, or ultrasound techniques were recommended to assist in proper muscle localization for injections. The duration of follow-up was 12 weeks.

Table 40: BOTOX Dose and Injection Sites in Study 6
Muscles Injected | BOTOX 160 U (Units) | Volume (mL) | Number of Injection Sites
Elbow Biceps Brachii | 70 | 1.4 | 2
Brachioradialis | 45 | 0.9 | 1
Brachialis | 45 | 0.9 | 1

The change from baseline in elbow flexor tone measured by modified Ashworth Scale at Week 6 is presented in Table 41.

Table 41: Primary Efficacy Endpoint Results for Elbow Flexors at Week 6 in Study 6
 | BOTOX 160 U (N=61) | Placebo (N=63)
Mean Change from Baseline in Elbow Flexor Muscle Tone on the modified Ashworth Scale at Week 6 | -1.09* | -0.71

*nominal p value <0.05

Adult Lower Limb Spasticity

The efficacy and safety of BOTOX for the treatment of adult lower limb spasticity was evaluated in Study 7, a randomized, multi-center, double-blind, placebo-controlled study. Study 7 included 468 post-stroke adult patients (233 BOTOX and 235 placebo) with ankle spasticity (modified Ashworth Scale ankle score of at least 3) who were at least 3 months post-stroke. A total dose of 300 Units of BOTOX or placebo were injected intramuscularly and divided between the gastrocnemius, soleus, and tibialis posterior, with optional injection into the flexor hallucis longus, flexor digitorum longus, flexor digitorum brevis, extensor hallucis, and rectus femoris (see Table 42) with up to an additional 100 Units (400 Units total dose). The use of electromyographic guidance or nerve stimulation was required to assist in proper muscle localization for injections. Patients were followed for 12 weeks.

Table 42: BOTOX Dose and Injection Sites in Study 7
Muscles Injected | BOTOX (Units) | Numberof Injection Sites
Mandatory Ankle Muscles Gastrocnemius (medial head) | 75 | 3
Gastrocnemius (lateral head) | 75 | 3
Soleus | 75 | 3
Tibialis Posterior | 75 | 3
Optional Muscles Flexor Hallucis Longus | 50 | 2
Flexor Digitorum Longus | 50 | 2
Flexor Digitorum Brevis | 25 | 1
Extensor Hallucis | 25 | 1
Rectus Femoris | 100 | 4

The co-primary endpoints were the average of the change from baseline in modified Ashworth Scale (MAS) ankle score at Week 4 and Week 6, and the average of the Physician Global Assessment of Response (CGI) at Week 4 and Week 6. The CGI evaluated the response to treatment in terms of how the patient was doing in his/her life using a 9-point scale from -4=very marked worsening to +4=very marked improvement.

Statistically significant between-group differences for BOTOX over placebo were demonstrated for the co-primary efficacy measures of MAS and CGI (see Table 43).

Table 43: Co-Primary Efficacy Endpoints Results in Study 7 (Intent-To-Treat Population)
 | BOTOX 300 to 400 Units (N=233) | Placebo (N=235)
Mean Change from Baseline in Ankle Plantar Flexors on the modified Ashworth Scale
Week 4 and 6 Average | -0.8* | -0.6
Mean Clinical Global Impression Score by Investigator
Week 4 and 6 Average | 0.9* | 0.7

*Significantly different from placebo (p<0.05)

Compared to placebo, significant improvements in MAS change from baseline for ankle plantar flexors (see Figure 13) and CGI (see Figure 14) were observed at Week 2, Week 4, and Week 6 for patients treated with BOTOX.

Figure 13: Modified Ashworth Scale Ankle Scorefor Study 7–Mean Change from Baseline by Visit

Figure 14: Clinical Global Impression by Physicianfor Study 7–Mean Scores by Visit

14.6 Pediatric Spasticity

Pediatric Upper Limb Spasticity

The efficacy and safety of BOTOX for the treatment of upper limb spasticity in pediatric patients 2 to 17 years of age was evaluated in Study 1 (NCT01603602), a randomized, multi-center, double-blind, placebo-controlled study. Study 1 included 234 pediatric patients (78 BOTOX 3 Units/kg, 77 BOTOX 6 Units/kg, and 79 placebo) with upper limb spasticity (modified Ashworth Scale elbow or wrist score of at least 2) because of cerebral palsy or stroke. A total dose of 3 Units/kg BOTOX (maximum 100 Units), 6 Units/kg BOTOX (maximum 200 Units), or placebo was injected intramuscularly and divided between the elbow or wrist and finger muscles (see Table 44). Electromyographic guidance, nerve stimulation, or ultrasound techniques were used to assist in muscle localization for injections. Patients were followed for 12 weeks after injection.

Table 44: BOTOX Dose and Injection Sites in Study 1
Muscles Injected | BOTOX 3 Units/kg* (maximum Units per muscle) | BOTOX 6 Units/kg** (maximum Units per muscle) | Number of Injection Sites
Elbow Flexor Muscles
Biceps | 1.5 Units/kg (50 Units) | 3 Units/kg (100 Units) | 4
Brachialis | 1 Unit/kg (30 Units) | 2 Units/kg (60 Units) | 2
Brachioradialis | 0.5 Units/kg (20 Units) | 1 Unit/kg (40 Units) | 2
Wrist and Finger Muscles
Flexor carpi radialis | 1 Unit/kg (25 Units) | 2 Units/kg (50 Units) | 2
Flexor carpi ulnaris | 1 Unit/kg (25 Units) | 2 Units/kg (50 Units) | 2
Flexor digitorum profundus | 0.5 Units/kg (25 Units) | 1 Unit/kg (50 Units) | 2
Flexor digitorum sublimis | 0.5 Units/kg (25 Units) | 1 Unit/kg (50 Units) | 2

* Did not exceed a total dose of 100 Units

** Did not exceed a total dose of 200 Units

The co-primary endpoints were the average of the change from baseline in modified Ashworth Scale (MAS) principal muscle group score (elbow or wrist) at Week 4 and Week 6, and the average of the Clinical Global Impression of Overall Change by Physician (CGI) at Week 4 and Week 6. The CGI evaluated the response to treatment in terms of how the patient was doing in his/her life using a 9-point scale (-4=very marked worsening to +4=very marked improvement).

Compared to placebo, significant improvements in MAS change from baseline were observed at all timepoints for BOTOX-treated patients (see Table 45, Figure 15 and Figure 16). Although CGI scores numerically favored BOTOX over placebo, the difference was not statistically significant.

Table 45: Co-Primary Efficacy Endpoints Results in Study 1 (Pediatric Upper Limb Spasticity, Modified Intent-To-Treat Population)
 | BOTOX 3 Units/kg (N=78) | BOTOX 6 Units/kg (N=77) | Placebo (N=79)
Mean Change from Baseline in Principal Muscle Group (Elbow or Wrist) on the modified Ashworth Scale
Week 4 and 6 Average | -1.92* | -1.87* | -1.21
Mean Clinical Global Impression Score
Week 4 and 6 Average | 1.88 | 1.87 | 1.66

*Nominal p value <0.05

Figure 15: Modified Ashworth Scale Score for Study 1 (Pediatric Upper Limb Spasticity, Modified Intent-To-Treat Population) – Mean Change from Baseline by Visit

Figure 16: Clinical Global Impression of Overall Change for Study 1 (Pediatric Upper Limb Spasticity, Modified Intent-To-Treat Population) – Mean Scores by Visit

Pediatric Lower Limb Spasticity

The efficacy and safety of BOTOX for the treatment of lower limb spasticity in pediatric patients 2 to 17 years of age was evaluated in Study 2 (NCT01603628), a randomized, multi-center, double-blind, placebo-controlled study. Study 2 included 381 pediatric patients (125 BOTOX 4 Units/kg, 127 BOTOX 8 Units/kg, and 129 placebo) with lower limb spasticity (modified Ashworth Scale ankle score of at least 2) because of cerebral palsy. A total dose of 4 Units/kg BOTOX (maximum 150 Units), 8 Units/kg BOTOX (maximum 300 Units), or placebo was injected intramuscularly and divided between the gastrocnemius, soleus, and tibialis posterior (see Table 46). Electromyographic guidance, nerve stimulation, or ultrasound techniques were used to assist in muscle localization for injections. Patients were followed for 12 weeks after injection.

Table 46: BOTOX Dose and Injection Sites in Study 2
Muscles Injected | BOTOX 4 Units/kg* (maximum Units per muscle) | BOTOX 8 Units/kg** (maximum Units per muscle) | Numberof Injection Sites
Mandatory Ankle Muscles Gastrocnemius medial head | 1 Unit/kg (37.5 Units) | 2 Units/kg (75 Units) | 2
Gastrocnemius lateral head | 1 Unit/kg (37.5 Units) | 2 Units/kg (75 Units) | 2
Soleus | 1 Unit/kg (37.5 Units) | 2 Units/kg (75 Units) | 2
Tibialis Posterior | 1 Unit/kg (37.5 Units) | 2 Units/kg (75 Units) | 2

* did not exceed a total dose of 150 Units

** did not exceed a total dose of 300 Units

The co-primary endpoints were the average of the change from baseline in modified Ashworth Scale (MAS) ankle score at Week 4 and Week 6, and the average of the Clinical Global Impression of Overall Change by Physician (CGI) at Week 4 and Week 6. The CGI evaluated the response to treatment in terms of how the patient was doing in his/her life using a 9-point scale (-4=very marked worsening to +4=very marked improvement).

Statistically significant differences between BOTOX and placebo were demonstrated for the MAS and CGI for the 8 Units/kg dose only (see Table 47).

Table 47: Co-Primary Efficacy Endpoints Results in Study 2 (Pediatric Lower Limb Spasticity, Modified Intent-To-Treat Population)
 | BOTOX 4 Units/kg (N = 125) | BOTOX 8 Units/kg (N=127) | Placebo (N=129)
Mean Change from Baseline in Plantar Flexors on the modified Ashworth Scale
Week 4 and 6 Average | -1.01** | -1.06* | -0.80
Mean Clinical Global Impression Score
Week 4 and 6 Average | 1.49 | 1.65* | 1.36

* Significantly different from placebo (p<0.05)

** Nominal p value <0.05

Compared to placebo, improvements in mean change from baseline for the MAS, and mean CGI score for lower limb spasticity were observed at timepoints up to Week 12 for BOTOX-treated patients (see Figure 17and Figure 18).

Figure 17: Modified Ashworth Scale Ankle Score for Study 2 (Pediatric Lower Limb Spasticity, Modified Intent-To-Treat Population) – Mean Change from Baseline by Visit

Figure 18: Clinical Global Impression of Overall Change for Study 2 (Pediatric Lower Limb Spasticity, Modified Intent-To-Treat Population) – Mean Scores by Visit

14.7 Cervical Dystonia

A randomized, multi-center, double-blind, placebo-controlled study of the treatment of cervical dystonia was conducted. This study enrolled adult patients with cervical dystonia and a history of having received BOTOX in an open label manner with perceived good response and tolerable side effects. Patients were excluded if they had previously received surgical or other denervation treatment for their symptoms or had a known history of neuromuscular disorder. Subjects participated in an open label enrichment period where they received their previously employed dose of BOTOX. Only patients who were again perceived as showing a response were advanced to the randomized evaluation period. The muscles in which the blinded study agent injections were to be administered were determined on an individual patient basis.

There were 214 subjects evaluated for the open label period, of which 170 progressed into the randomized, blinded treatment period (88 in the BOTOX group, 82 in the placebo group). Patient evaluations continued for at least 10 weeks post-injection. The primary outcome for the study was a dual endpoint, requiring evidence of both a change in the Cervical Dystonia Severity Scale (CDSS) and an increase in the percentage of patients showing any improvement on the Physician Global Assessment Scale at 6 weeks after the injection session. The CDSS quantifies the severity of abnormal head positioning and was newly devised for this study. CDSS allots 1 point for each 5 degrees (or part thereof) of head deviation in each of the three planes of head movement (range of scores up to theoretical maximum of 54). The Physician Global Assessment Scale is a 9 category scale scoring the physician’s evaluation of the patients’ status compared to baseline, ranging from –4 to +4 (very marked worsening to complete improvement), with 0 indicating no change from baseline and +1 slight improvement. Pain is also an important symptom of cervical dystonia and was evaluated by separate assessments of pain frequency and severity on scales of 0 (no pain) to 4 (constant in frequency or extremely severe in intensity). Study results on the primary endpoints and the pain-related secondary endpoints are shown in Table 48.

Table 48: Efficacy Outcomes of the Phase 3 Cervical Dystonia Study (Group Means)
 | Placebo (N=82) | BOTOX (N=88) | 95% CI on Difference
Baseline CDSS | 9.3 | 9.2
Change in CDSS at Week 6 | -0.3 | -1.3 | (-2.3, 0.3)[a,b]
% Patients with Any Improvement on Physician Global Assessment | 31% | 51% | (5%, 34%)[a]
Pain Intensity Baseline | 1.8 | 1.8
Change in Pain Intensity at Week 6 | -0.1 | -0.4 | (-0.7, -0.2)[c]
Pain Frequency Baseline | 1.9 | 1.8
Change in Pain Frequency at Week 6 | -0.0 | -0.3 | (-0.5, -0.0)[c]

[a]Confidence intervals are constructed from the analysis of covariance table with treatment and investigational site as main effects, and baseline CDSS as a covariate.

[b]These values represent the prospectively planned method for missing data imputation and statistical test. Sensitivity analyses indicated that the 95% confidence interval excluded the value of no difference between groups and the p-value was less than 0.05. These analyses included several alternative missing data imputation methods and non-parametric statistical tests.

[c]Confidence intervals are based on the t-distribution.

Exploratory analyses of this study suggested that the majority of patients who had shown a beneficial response by week 6 had returned to their baseline status by 3 months after treatment. Exploratory analyses of subsets by patient sex and age suggest that both sexes receive benefit, although female patients may receive somewhat greater amounts than male patients. There is a consistent treatment-associated effect between subsets greater than and less than age 65. There were too few non-Caucasian patients enrolled to draw any conclusions regarding relative efficacy in racial subsets.

In this study the median total BOTOX dose in patients randomized to receive BOTOX (N=88) was 236 Units, with 25th to 75th percentile ranges of 198 Units to 300 Units. Of these 88 patients, most received injections to 3 or 4 muscles; 38 received injections to 3 muscles, 28 to 4 muscles, 5 to 5 muscles, and 5 to 2 muscles. The dose was divided amongst the affected muscles in quantities shown in Table 49. The total dose and muscles selected were tailored to meet individual patient needs.

Table 49: Number of Patients Treated per Muscle and Fraction of Total Dose Injected into Involved Muscles
Muscle | Number of Patients Treated in this Muscle (N=88) | Mean % Dose per Muscle | Mid-Range of % Dose per Muscle*
Splenius capitis/cervicis | 83 | 38 | 25-50
Sternocleidomastoid | 77 | 25 | 17-31
Levator scapulae | 52 | 20 | 16-25
Trapezius | 49 | 29 | 18-33
Semispinalis | 16 | 21 | 13-25
Scalene | 15 | 15 | 6-21
Longissimus | 8 | 29 | 17-41

* The mid-range of dose is calculated as the 25th to 75th percentiles.

There were several randomized studies conducted prior to the double-blind, placebo-controlled study, which were supportive but not adequately designed to assess or quantitatively estimate the efficacy of BOTOX.

14.8 Primary Axillary Hyperhidrosis

The efficacy and safety of BOTOX for the treatment of primary axillary hyperhidrosis were evaluated in two randomized, multi-center, double-blind, placebo-controlled studies. Study 1 included adult patients with persistent primary axillary hyperhidrosis who scored 3 or 4 on a Hyperhidrosis Disease Severity Scale (HDSS) and who produced at least 50 mg of sweat in each axilla at rest over 5 minutes. HDSS is a 4-point scale with 1 = “underarm sweating is never noticeable and never interferes with my daily activities”; to 4 = “underarm sweating is intolerable and always interferes with my daily activities”. A total of 322 patients were randomized in a 1:1:1 ratio to treatment in both axillae with either 50 Units of BOTOX, 75 Units of BOTOX, or placebo. Patients were evaluated at 4-week intervals. Patients who responded to the first injection were re-injected when they reported a re-increase in HDSS score to 3 or 4 and produced at least 50 mg sweat in each axilla by gravimetric measurement, but no sooner than 8 weeks after the initial injection.

Study responders were defined as patients who showed at least a 2-grade improvement from baseline value on the HDSS 4 weeks after both of the first two treatment sessions or had a sustained response after their first treatment session and did not receive re-treatment during the study. Spontaneous resting axillary sweat production was assessed by weighing a filter paper held in the axilla over a period of 5 minutes (gravimetric measurement). Sweat production responders were those patients who demonstrated a reduction in axillary sweating from baseline of at least 50% at week 4.

In the three study groups the percentage of patients with baseline HDSS score of 3 ranged from 50% to 54% and from 46% to 50% for a score of 4. The median amount of sweat production (averaged for each axilla) was 102 mg, 123 mg, and 114 mg for the placebo, 50 Units and 75 Units groups respectively.

The percentage of responders based on at least a 2-grade decrease from baseline in HDSS or based on a >50% decrease from baseline in axillary sweat production was greater in both BOTOX groups than in the placebo group (p<0.001), but was not significantly different between the two BOTOX doses (see Table 50).

Duration of response was calculated as the number of days between injection and the date of the first visit at which patients returned to 3 or 4 on the HDSS scale. The median duration of response following the first treatment in BOTOX treated patients with either dose was 201 days. Among those who received a second BOTOX injection, the median duration of response was similar to that observed after the first treatment.

In study 2, 320 adults with bilateral axillary primary hyperhidrosis were randomized to receive either 50 Units of BOTOX (n=242) or placebo (n=78). Treatment responders were defined as subjects showing at least a 50% reduction from baseline in axillary sweating measured by gravimetric measurement at 4 weeks. At week 4 post-injection, the percentages of responders were 91% (219/242) in the BOTOX group and 36% (28/78) in the placebo group, p<0.001. The difference in percentage of responders between BOTOX and placebo was 55% (95% CI=43.3, 65.9).

Table 50: Study 1 - Study Outcomes
Treatment Response | BOTOX 50 Units (N=104) | BOTOX 75 Units (N=110) | Placebo (N=108) | BOTOX 50-placebo (95% CI) | BOTOX 75-placebo (95% CI)
HDSS Score change≥2 (n) a | 55% (57) | 49% (54) | 6% (6) | 49.3% (38.8, 59.7) | 43% (33.2, 53.8)
>50% decrease in axillary sweat production % (n) | 81% (84) | 86% (94) | 41% (44) | 40% (28.1, 52.0) | 45% (33.3, 56.1)

aPatients who showed at least a 2-grade improvement from baseline value on the HDSS 4 weeks after both of the first two treatment sessions or had a sustained response after their first treatment session and did not receive re-treatment during the study.

14.9 Blepharospasm

Botulinum toxin has been investigated for use in patients with blepharospasm in several studies. In an open label, historically controlled study, 27 patients with essential blepharospasm were injected with 2 Units of BOTOX at each of six sites on each side. Twenty-five of the 27 patients treated with botulinum toxin reported improvement within 48 hours. One patient was controlled with a higher dosage at 13 weeks post initial injection and one patient reported mild improvement but remained functionally impaired.

In another study, 12 patients with blepharospasm were evaluated in a double-blind, placebo-controlled study. Patients receiving botulinum toxin (n=8) improved compared with the placebo group (n=4). The effects of the treatment lasted a mean of 12 weeks.

One thousand six hundred eighty-four patients with blepharospasm who were evaluated in an open label trial showed clinical improvement as evaluated by measured eyelid force and clinically observed intensity of lid spasm, lasting an average of 12 weeks prior to the need for re-treatment.

14.10 Strabismus

Six hundred seventy-seven patients with strabismus treated with one or more injections of BOTOX were evaluated in an open label trial. Fifty-five percent of these patients improved to an alignment of 10 prism diopters or less when evaluated six months or more following injection.

16 HOW SUPPLIED/STORAGE AND HANDLING

16.1 How Supplied

BOTOX (onabotulinumtoxinA) for injection is a sterile, vacuum-dried powder supplied in a single-dose vial in the following sizes:

100 Units NDC 85766-155-01 (relabeled from NDC 0023-1145-01) and NDC 85766-155-02 (relabeled from NDC 0023-1145-02)

BOTOX cartons have features to alert users if contents may have been compromised. Each BOTOX vial label and carton also contains the U.S. License number: 1889 [see Dosage and Administration (2.1)].

Do not use the product and contact AbbVie for additional information at 1-800-678-1605 if the labeling is not described as above.

16.2 Storage and Handling

Unopened vials of BOTOX should be stored in a refrigerator between 2° to 8°C (36º to 46ºF) for up to 36 months. Do not use after the expiration date on the vial. Reconstituted BOTOX may be stored in a refrigerator (2° to 8°C) for up to 24 hours until time of use [see Dosageand Administration (2.2)].

17 PATIENT COUNSELING INFORMATION

Advise the patient or caretaker to read the FDA-approved patient labeling (Medication Guide).

Swallowing, Speaking or Breathing Difficulties, or Other Unusual Symptoms

Advise patients or their caretaker(s) to inform their doctor or pharmacist if they develop any unusual symptoms (including difficulty with swallowing, speaking, or breathing), or if any existing symptom worsens [see Boxed Warningand Warnings and Precautions (5.1,5.6)].

Ability to Operate Machinery or Vehicles

Advise patients or their caretaker(s) that if loss of strength, muscle weakness, blurred vision, dizziness, or drooping eyelids occur, they should avoid driving a car or engaging in other potentially hazardous activities.

Voiding Symptoms after Bladder Injections

After bladder injections for urinary incontinence, advise patients to contact their physician if they experience difficulties in voiding or burning sensation upon voiding.

Distributed by:

Sportpharm LLC

379 Van Ness Ave 1401,

Torrance, CA 90501

Relabeled by:

Enovachem PHARMACEUTICALS

Torrance, CA 90501

All rights reserved.

BOTOX and its design are trademarks of Allergan Inc., an AbbVie company.

Patented. See: https://www.abbvie.com/patents.html

MEDICATION GUIDE
BOTOX®
BOTOX® Cosmetic
(Boe-tox)
(onabotulinumtoxinA)
forinjection, for intramuscular, intradetrusor,
or intradermaluse

What is the most important information I should know about BOTOXand BOTOX Cosmetic?
BOTOX and BOTOX Cosmetic may cause serious side effects that can be life threatening, including:

- Problems breathing or swallowing
- Spread of toxin effects

These problems can happen hours, days, to weeks after an injection of BOTOX or BOTOX Cosmetic. Call your doctor or get medical help right away if you have any of these problems after treatment with BOTOXor BOTOXCosmetic:

- Problems swallowing, speaking, or breathing. These problems can happen hours, days, to weeks after an injection of BOTOXor BOTOX Cosmeticusually because the muscles that you use to breathe and swallow can become weak after the injection. Death can happen as a complication if you have severe problems with swallowing or breathing after treatment with BOTOXor BOTOXCosmetic.
  - People with certain breathing problems may need to use muscles in their neck to help them breathe. These people may be at greater risk for serious breathing problems with BOTOXor BOTOXCosmetic.
  - Swallowing problems may last for several months. People who cannot swallow well may need a feeding tube to receive food and water. If swallowing problems are severe, food or liquids may go into your lungs. People who already have swallowing or breathing problems before receiving BOTOXor BOTOXCosmetichave the highest risk of getting these problems.
- Spread of toxin effects.In some cases, the effect of botulinum toxin may affect areas of the body away from the injection site and cause symptoms of a serious condition called botulism. The symptoms of botulism include:
  ○ loss of strength and muscle weakness all over the body
  ○ double vision, blurred vision and drooping eyelids
  ○ hoarseness or change or loss of voice (dysphonia)
  ○ trouble saying words clearly (dysarthria)
  ○ loss of bladder control
  ○ trouble breathing
  ○ trouble swallowing

These symptoms can happen hours, days, to weeks after you receive an injection of BOTOXor BOTOXCosmetic.
These problems could make it unsafe for you to drive a car or do other dangerous activities. See "What should I avoid while receiving BOTOXor BOTOXCosmetic?"
There has not been a confirmed serious case of spread of toxin effect away from the injection site when BOTOXhas been used at the recommended dose to treat chronic migraine, severe underarm sweating, blepharospasm, or strabismus, or when BOTOX Cosmetichas been used at the recommended dose to treat frown lines, crow’s feet lines, forehead lines, or vertical bands connecting the jaw and neck.

What are BOTOX and BOTOX Cosmetic?
BOTOXis a prescription medicine that is injected into muscles and used:

- to treat overactive bladder symptoms such as a strong need to urinate with leaking or wetting accidents (urge urinary incontinence), a strong need to urinate right away (urgency) and urinating often (frequency) in adults when another type of medicine (anticholinergic) does not work well enough or cannot be taken.
- to treat leakage of urine (incontinence) in adults with overactive bladder due to neurologic disease when another type of medicine (anticholinergic) does not work well enough or cannot be taken.
- to treat overactive bladder due to a neurologic disease in children 5 years of age and older when another type of medicine (anticholinergic) does not work well enough or cannot be taken.
- to prevent headaches in adults with chronic migraine who have 15 or more days each month with headache lasting 4 or more hours each day.
- to treat increased muscle stiffness in people 2 years of age and older with spasticity.
- to treat the abnormal head position and neck pain that happens with cervical dystonia (CD) in adults.
- to treat certain types of eye muscle problems (strabismus) or abnormal spasm of the eyelids (blepharospasm) in people 12 years of age and older.

BOTOXis also injected into the skin to treat the symptoms of severe underarm sweating (severe primary axillary hyperhidrosis) when medicines used on the skin (topical) do not work well enough.

BOTOXCosmeticis a prescription medicine for adults that is injected into muscles and used for a short period of time (temporary) to improve the look of:

- moderate to severe frown lines between the eyebrows (glabellar lines)
- moderate to severe crow’s feet lines
- moderate to severe forehead lines
- moderate to severe vertical bands connecting the jaw and neck (platysma bands)

You may receive treatment for frown lines, crow’s feet lines, forehead lines, and vertical bands connecting the jaw and neck at the same time.

It is not known whether BOTOXis safe and effective in people younger than:

- 18 years of age for treatment of overactive bladder with urinary incontinence
- 5 years of age for the treatment of overactive bladder due to a neurologic disease
- 18 years of age for treatment of chronic migraine
- 16 years of age for treatment of cervical dystonia
- 18 years of age for treatment of hyperhidrosis
- 12 years of age for treatment of strabismus or blepharospasm
- 2 years of age for treatment of spasticity

BOTOXCosmeticis not recommended for use in children younger than 18 years of age.
It is not known whether BOTOXand BOTOX Cosmeticare safe and effective to prevent headaches in people with migraine who have 14 or fewer headache days each month (episodic migraine).
It is not known whether BOTOXand BOTOXCosmeticare safe and effective for severe sweating anywhere other than your armpits.
It is not known if BOTOX Cosmeticis safe and effective for use more than 1 time every 3 months.

Who should notreceive BOTOXor BOTOX Cosmetic?
Do not receive BOTOXor BOTOXCosmeticif you:

- are allergic to any of the ingredients in BOTOXor BOTOXCosmetic. See the end of this Medication Guide for a complete list of ingredients in BOTOXand BOTOXCosmetic.
- had an allergic reaction to any other botulinum toxin product such as Myobloc ®(rimabotulinumtoxinB), Dysport®(abobotulinumtoxinA), Xeomin®(incobotulinumtoxinA), Jeuveau®(prabotulinumtoxinA-xvfs), Daxxify®(daxibotulinumtoxinA-lanm), or Letybo®(letibotulinumtoxinA-wlbg). This may not be a complete list of all botulinum toxin products.
- have a skin infection at the planned injection site.
- are being treated for urinary incontinence and have a urinary tract infection (UTI).
- are being treated for urinary incontinence and find that you cannot empty your bladder on your own (only applies to people who are not routinely catheterizing).

What should I tell my doctor beforereceiving BOTOX or BOTOX Cosmetic?
Tell your doctor about all your medical conditions, including if you:

- have a disease that affects your muscles and nerves (such as amyotrophic lateral sclerosis [ALS or Lou Gehrig's disease], myasthenia gravis or Lambert-Eaton syndrome). See "What is the most important information I should know about BOTOXand BOTOXCosmetic?"
- have allergies to any botulinum toxin product.
- had any side effect from any botulinum toxin product in the past.
- have or have had a breathing problem, such as asthma or emphysema.
- have or have had swallowing problems.
- have or have had bleeding problems.
- have plans to have surgery.
- had surgery on your face.
- have weakness of your forehead muscles, such as trouble raising your eyebrows.
- have drooping eyelids.
- have any other change in the way your face normally looks.
- have symptoms of a urinary tract infection (UTI) and are being treated for urinary incontinence. Symptoms of a urinary tract infection may include pain or burning with urination, frequent urination, or fever.
- have problems emptying your bladder on your own and are being treated for urinary incontinence.
- are pregnant or plan to become pregnant. It is not known if BOTOXor BOTOXCosmeticcan harm your unborn baby.
- are breastfeeding or plan to breastfeed. It is not known if BOTOXor BOTOXCosmetic passes into breast milk.

Tell your doctor about all the medicines you take, including prescription and over-the-counter medicines, vitamins and herbal supplements. Using BOTOXor BOTOXCosmeticwith certain other medicines may cause serious side effects. Do not start any new medicines until you have told your doctor that you have received BOTOX or BOTOX Cosmetic in the past.
Especially tell your doctor if you:

- have received any other botulinum toxin product in the last four months.
- have received injections of botulinum toxin, such as Myobloc ®(rimabotulinumtoxinB), Dysport®(abobotulinumtoxinA), Xeomin®(incobotulinumtoxinA), Jeuveau®(prabotulinumtoxinA-xvfs), Daxxify®(daxibotulinumtoxinA-lanm), or Letybo® (letibotulinumtoxinA-wlbg) in the past. This may not be a complete list of all botulinum toxin products. Be sure your doctor knows exactly which product you received.
- have recently received an antibiotic by injection.
- take muscle relaxants.
- take an allergy or cold medicine.
- take a sleep medicine.
- take anti-platelets (aspirin-like products) or anti-coagulants (blood thinners).

Ask your doctor if you are not sure if your medicine is one that is listed above.
Know the medicines you take. Keep a list of your medicines with you to show your doctor and pharmacist each time you get a new medicine.

Howwill Ireceive BOTOX or BOTOX Cosmetic?

- BOTOXor BOTOXCosmeticis an injection that your doctor will give you.
- BOTOX is injected into your affected muscles, skin, or bladder.
- BOTOXCosmeticis injected into your affected muscles.
- Your doctor may change your dose of BOTOXor BOTOXCosmetic, until you and your doctor find the best dose for you.
- Your doctor will tell you how often you will receive your dose of BOTOX or BOTOX Cosmetic injections.

What should I avoid whilereceiving BOTOX or BOTOX Cosmetic?
BOTOXand BOTOXCosmeticmay cause loss of strength or general muscle weakness, vision problems, or dizziness within hours to weeks of taking BOTOXor BOTOXCosmetic. If this happens, do not drive a car, operate machinery, or do other dangerous activities.See "What is the most important information I should know about BOTOXand BOTOXCosmetic?"

What are the possible side effects of BOTOX and BOTOX Cosmetic?
BOTOXand BOTOX Cosmetic can cause serious side effects.See "What is the most important information I should know about BOTOXand BOTOXCosmetic?"
Other side effects of BOTOX and BOTOX Cosmetic include:

- dry mouth.
- discomfort or pain at the injection site.
- tiredness.
- headache.
- neck pain.
- eye problems: double vision, blurred vision, decreased eyesight, drooping eyelids, swelling of your eyelids, and dry eyes.
- drooping eyebrows.
- urinary tract infection in both children and adults being treated for urinary incontinence.
- painful urination in adults being treated for urinary incontinence.
- bacteria, white blood cells, and blood in the urine of children being treated for urinary incontinence.
- inability to empty your bladder on your own and are being treated for urinary incontinence. If you have difficulty fully emptying your bladder after getting BOTOX, you may need to use disposable self-catheters to empty your bladder up to a few times each day until your bladder is able to start emptying again.
- allergic reactions. Symptoms of an allergic reaction to BOTOXor BOTOXCosmeticmay include: itching, rash, red itchy welts, wheezing, asthma symptoms, or dizziness or feeling faint. Tell your doctor or get medical help right away if you are wheezing or have asthma symptoms, or if you become dizzy or faint.
- upper respiratory tract infection.

Tell your doctor if you have any side effect that bothers you or that does not go away.
These are not all the possible side effects of BOTOXand BOTOXCosmetic. For more information, ask your doctor or pharmacist.
Call your doctor for medical advice about side effects. You may report side effects to FDA at 1-800-FDA-1088.

General information aboutthe safe and effective use of BOTOX and BOTOX Cosmetic:
Medicines are sometimes prescribed for purposes other than those listed in a Medication Guide.
This Medication Guide summarizes the most important information about BOTOXand BOTOXCosmetic. If you would like more information, talk with your doctor. You can ask your doctor or pharmacist for information about BOTOXand BOTOXCosmeticthat is written for health professionals.

What are the ingredients in BOTOX and BOTOX Cosmetic?
Active ingredient: onabotulinumtoxinA
Inactive ingredients: human albumin and sodium chloride

Distributed by:

Sportpharm LLC

379 Van Ness Ave 1401,

Torrance, CA 90501

Relabeled by:

Enovachem PHARMACEUTICALS

Torrance, CA 90501

U.S. License Number 1889
© 2024 AbbVie. All rights reserved. BOTOX and its design are trademarks of Allergan Inc., an AbbVie company.

All trademarks are the property of their respective owners.

V8.0MG1145

This Medication Guide has been approved by the U.S. Food and Drug Administration Revised: 10/2024